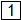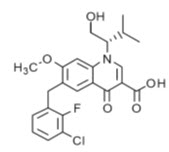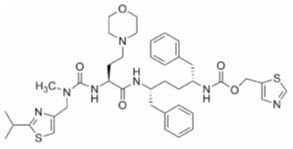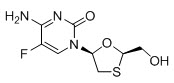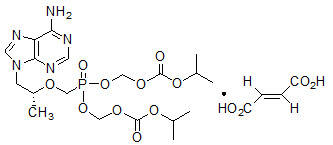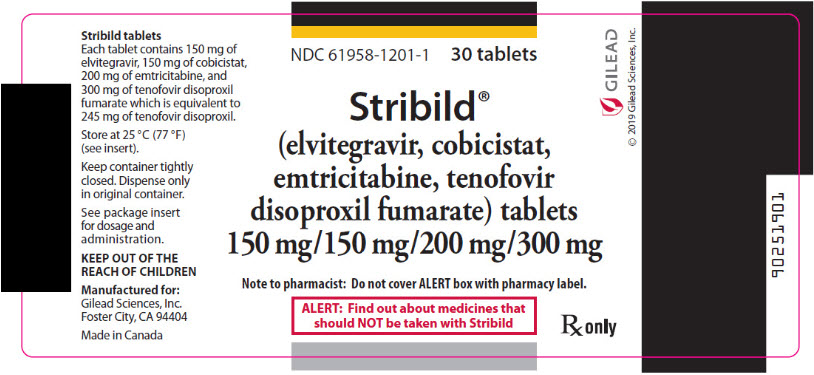 DRUG LABEL: Stribild
NDC: 61958-1201 | Form: TABLET, FILM COATED
Manufacturer: Gilead Sciences, Inc.
Category: prescription | Type: HUMAN PRESCRIPTION DRUG LABEL
Date: 20250204

ACTIVE INGREDIENTS: elvitegravir 150 mg/1 1; cobicistat 150 mg/1 1; emtricitabine 200 mg/1 1; tenofovir disoproxil fumarate 300 mg/1 1
INACTIVE INGREDIENTS: MICROCRYSTALLINE CELLULOSE; CROSCARMELLOSE SODIUM; MAGNESIUM STEARATE; SILICON DIOXIDE; SODIUM LAURYL SULFATE; LACTOSE MONOHYDRATE; HYDROXYPROPYL CELLULOSE (1600000 WAMW); POLYVINYL ALCOHOL, UNSPECIFIED; POLYETHYLENE GLYCOL, UNSPECIFIED; TITANIUM DIOXIDE; TALC; FD&C BLUE NO. 2; ALUMINUM OXIDE; FERRIC OXIDE YELLOW

HIGHLIGHTS OF PRESCRIBING INFORMATION

These highlights do not include all the information needed to use STRIBILD safely and effectively. See full prescribing information for STRIBILD.
STRIBILD® (elvitegravir, cobicistat, emtricitabine, tenofovir disoproxil fumarate) tablets, for oral use
Initial U.S. Approval: 2012

WARNING: POSTTREATMENT ACUTE EXACERBATION OF HEPATITIS B

See full prescribing information for complete boxed warning.

Severe acute exacerbations of hepatitis B have been reported in patients coinfected with HIV-1 and HBV who have discontinued EMTRIVA or VIREAD, two of the components of STRIBILD. Hepatic function should be monitored closely in these patients. If appropriate, initiation of anti-hepatitis B therapy may be warranted. (5.1)

1 INDICATIONS AND USAGE

STRIBILD is a four-drug combination of elvitegravir, an HIV integrase strand transfer inhibitor (HIV-1 INSTI), cobicistat, a CYP3A inhibitor, and emtricitabine and tenofovir disoproxil fumarate (TDF), both HIV nucleoside analog reverse transcriptase inhibitors (HIV NRTI) and is indicated as a complete regimen for the treatment of HIV-1 infection in adults and pediatric patients 12 years of age and older weighing at least 35 kg who have no antiretroviral treatment history or to replace the current antiretroviral regimen in those who are virologically suppressed (HIV-1 RNA less than 50 copies/mL) on a stable antiretroviral regimen for at least 6 months with no history of treatment failure and no known substitutions associated with resistance to the individual components of STRIBILD. (1, 14)

2 DOSAGE AND ADMINISTRATION

- Testing: Prior to initiation of STRIBILD, test patients for hepatitis B virus infection. Prior to initiation and during use of STRIBILD, on a clinically appropriate schedule, assess serum creatinine, serum phosphorous, estimated serum creatinine clearance, urine glucose, and urine protein in all patients. In patients with chronic kidney disease, also assess serum phosphorus. (2.1)
- Recommended dosage: One tablet taken once daily with food. (2.2)
- Dosage in renal impairment: Initiation of STRIBILD in patients with estimated creatinine clearance below 70 mL per minute is not recommended. Discontinue in patients with estimated creatinine clearance below 50 mL per minute. (2.3)

3 DOSAGE FORMS AND STRENGTHS

Tablets: 150 mg of elvitegravir, 150 mg of cobicistat, 200 mg of emtricitabine, and 300 mg of tenofovir disoproxil fumarate. (3)

4 CONTRAINDICATIONS

Coadministration of STRIBILD is contraindicated with drugs that:

- Are highly dependent on CYP3A for clearance and for which elevated plasma concentrations are associated with serious adverse events. (4)
- Strongly induce CYP3A, which may lead to lower exposure of one or more components and loss of efficacy of STRIBILD and possible resistance. (4)

5 WARNINGS AND PRECAUTIONS

- New onset or worsening renal impairment: Can include acute renal failure and Fanconi syndrome. Avoid administering STRIBILD with concurrent or recent use of nephrotoxic drugs. (5.2)
- Lactic acidosis/severe hepatomegaly with steatosis: Discontinue treatment in patients who develop symptoms or laboratory findings suggestive of lactic acidosis or pronounced hepatotoxicity. (5.3)
- Risk of adverse reactions or loss of virologic response due to drug interactions: The concomitant use of STRIBILD and other drugs may result in known or potentially significant drug interactions, some of which may lead to loss of therapeutic effect of STRIBILD and possible development of resistance; clinically significant adverse reactions from greater exposures of concomitant drugs; or loss of therapeutic effect of concomitant drugs. (5.4)
- Decreases in bone mineral density (BMD): Consider monitoring BMD in patients with a history of pathologic fracture or other risk factors of osteoporosis or bone loss. (5.5)
- Immune reconstitution syndrome: May necessitate further evaluation and treatment. (5.6)

6 ADVERSE REACTIONS

Most common adverse drug reactions to STRIBILD (incidence greater than or equal to 10%, all grades) are nausea and diarrhea. (6.1)

To report SUSPECTED ADVERSE REACTIONS, contact Gilead Sciences, Inc. at 1-800-GILEAD-5 or FDA at 1-800-FDA-1088 or www.fda.gov/medwatch.

7 DRUG INTERACTIONS

- STRIBILD is a complete regimen for the treatment of HIV-1 infection; therefore, STRIBILD should not be administered with other antiretroviral medications for treatment of HIV-1 infection. (7.1)
- STRIBILD can alter the concentration of drugs metabolized by CYP3A or CYP2D6. Drugs that induce CYP3A can alter the concentrations of one or more components of STRIBILD. Consult the full prescribing information prior to and during treatment for potential drug-drug interactions. (4, 7.2, 7.3, 12.3)

8 USE IN SPECIFIC POPULATIONS

- Pregnancy: Not recommended for use during pregnancy because of substantially lower exposures of cobicistat and elvitegravir during pregnancy. STRIBILD should not be initiated in pregnant individuals. (2.5, 8.1)
- Lactation: Breastfeeding is not recommended due to the potential for HIV transmission. (8.2)
- Pediatrics: Not recommended for patients less than 12 years of age or weighing less than 35 kg. (8.4)

FULL PRESCRIBING INFORMATION

WARNING: POSTTREATMENT ACUTE EXACERBATION OF HEPATITIS B

Severe acute exacerbations of hepatitis B have been reported in patients who are coinfected with HIV-1 and HBV and have discontinued EMTRIVA or VIREAD, which are components of STRIBILD. Hepatic function should be monitored closely, with both clinical and laboratory follow-up for at least several months in patients who are coinfected with HIV-1 and HBV and discontinue STRIBILD. If appropriate, initiation of anti-hepatitis B therapy may be warranted [see Warnings and Precautions (5.1)].

1 INDICATIONS AND USAGE

STRIBILD® is indicated as a complete regimen for the treatment of HIV-1 infection in adults and pediatric patients 12 years of age and older weighing at least 35 kg who have no antiretroviral treatment history or to replace the current antiretroviral regimen in those who are virologically suppressed (HIV-1 RNA less than 50 copies/mL) on a stable antiretroviral regimen for at least 6 months with no history of treatment failure and no known substitutions associated with resistance to the individual components of STRIBILD [see Clinical Studies (14)].

2 DOSAGE AND ADMINISTRATION

2.1 Testing Prior to Initiation and During Treatment with STRIBILD

Prior to initiation of STRIBILD, test patients for hepatitis B virus infection [see Warnings and Precautions (5.1)].

Prior to initiation and during use of STRIBILD, on a clinically appropriate schedule, assess serum creatinine, estimated creatinine clearance, urine glucose, and urine protein in all patients. In patients with chronic kidney disease, also assess serum phosphorus [see Warnings and Precautions (5.2)].

2.2 Recommended Dosage

STRIBILD is a four-drug fixed dose combination product containing 150 mg of elvitegravir, 150 mg of cobicistat, 200 mg of emtricitabine, and 300 mg of TDF. The recommended dosage of STRIBILD is one tablet taken orally once daily with food in adults and pediatric patients 12 years of age and older with a body weight at least 35 kg and creatinine clearance greater than or equal to 70 mL per minute [see Clinical Pharmacology (12.3)].

2.3 Dosage Adjustment in Patients with Renal Impairment

Initiation of STRIBILD in patients with estimated creatinine clearance below 70 mL per minute is not recommended. Because STRIBILD is a fixed-dose combination tablet, STRIBILD should be discontinued if estimated creatinine clearance declines below 50 mL per minute during treatment with STRIBILD, as the dose interval adjustment required for emtricitabine and tenofovir disoproxil fumarate (DF) cannot be achieved [see Warnings and Precautions (5.2), Adverse Reactions (6.1), Use in Specific Populations (8.6), Clinical Pharmacology (12.3), and Clinical Studies (14)].

No data are available to make dose recommendations for pediatric patients with renal impairment.

2.4 Not Recommended in Patients with Severe Hepatic Impairment

STRIBILD is not recommended for use in patients with severe hepatic impairment [see Use in Specific Populations (8.7) and Clinical Pharmacology (12.3)].

2.5 Not Recommended During Pregnancy

STRIBILD is not recommended for use during pregnancy because of substantially lower exposures of cobicistat and elvitegravir during the second and third trimesters [see Use in Specific Populations (8.1)].

STRIBILD should not be initiated in pregnant individuals. An alternative regimen is recommended for individuals who become pregnant during therapy with STRIBILD [see Use in Specific Populations (8.1)].

3 DOSAGE FORMS AND STRENGTHS

Each STRIBILD tablet contains 150 mg of elvitegravir, 150 mg of cobicistat, 200 mg of emtricitabine, and 300 mg of TDF (equivalent to 245 mg of tenofovir disoproxil).

The tablets are green, capsule shaped, film coated, and debossed with "GSI" on one side and the number "1" surrounded by a square box () on the other side.

4 CONTRAINDICATIONS

Coadministration of STRIBILD is contraindicated with drugs that are highly dependent on CYP3A for clearance and for which elevated plasma concentrations are associated with serious and/or life-threatening events. These drugs and other contraindicated drugs (which may lead to reduced efficacy of STRIBILD and possible resistance) are listed below [see Drug Interactions (7.5) and Clinical Pharmacology (12.3)].

- Alpha 1-adrenoreceptor antagonist: alfuzosin
- Anticonvulsants: carbamazepine, phenobarbital, phenytoin
- Antimycobacterial: rifampin
- Antipsychotics: lurasidone, pimozide
- Ergot Derivatives: dihydroergotamine, ergotamine, methylergonovine
- Herbal Products: St. John's wort (Hypericum perforatum)
- Lipid-modifying Agents: lomitapide, lovastatin, simvastatin
- Phosphodiesterase-5 (PDE-5) Inhibitor: sildenafil when administered as Revatio® for the treatment of pulmonary arterial hypertension
- Sedative/hypnotics: triazolam, orally administered midazolam

5 WARNINGS AND PRECAUTIONS

5.1 Severe Acute Exacerbation of Hepatitis B in Patients Coinfected with HIV-1 and HBV

All patients with HIV-1 should be tested for the presence of hepatitis B virus (HBV) before initiating antiretroviral therapy [see Dosage and Administration (2.1)].

Severe acute exacerbations of hepatitis B (e.g., liver decompensated and liver failure) have been reported in patients who are coinfected with HIV-1 and HBV and have discontinued emtricitabine or TDF, two of the components of STRIBILD. Patients who are coinfected with HIV-1 and HBV should be closely monitored with both clinical and laboratory follow-up for at least several months after stopping treatment with STRIBILD. If appropriate, initiation of anti-hepatitis B therapy may be warranted, especially in patients with advanced liver disease or cirrhosis, since posttreatment exacerbation of hepatitis may lead to hepatic decompensation and liver failure.

5.2 New Onset or Worsening Renal Impairment

Renal impairment, including cases of acute renal failure and Fanconi syndrome (renal tubular injury with severe hypophosphatemia), has been reported with the use of TDF, a component of STRIBILD, and with the use of STRIBILD [see Adverse Reactions (6.2)].

In the clinical trials of STRIBILD over 144 weeks, 13 (1.9%) subjects in the STRIBILD group (N=701), 8 (2.3%) subjects in the atazanavir (ATV) + ritonavir (RTV) + TRUVADA® (emtricitabine 200 mg/TDF 300 mg) group (N=355), and no subjects in the ATRIPLA® (efavirenz 600 mg/emtricitabine 200 mg/TDF 300 mg) group (N=352) discontinued study drug due to a renal adverse reaction. Of these discontinuations, 8 in the STRIBILD group and 1 in the ATV+RTV+TRUVADA group occurred during the first 48 weeks. Four (0.6%) subjects who received STRIBILD developed laboratory findings consistent with proximal renal tubular dysfunction, leading to discontinuation of STRIBILD during the first 48 weeks of treatment. Two of the four subjects had renal impairment (i.e., estimated creatinine clearance less than 70 mL per minute) at baseline. The laboratory findings in these 4 subjects improved but did not completely resolve in all subjects upon discontinuation of STRIBILD. Renal replacement therapy was not required for these subjects. One (0.3%) subject who received ATV+RTV+TRUVADA developed laboratory findings consistent with proximal renal tubular dysfunction, leading to discontinuation of ATV+RTV+TRUVADA after Week 96.

STRIBILD should be avoided with concurrent or recent use of a nephrotoxic agent (e.g., high-dose or multiple nonsteroidal anti-inflammatory drugs [NSAIDs]) [see Drug Interactions (7.4)]. Cases of acute renal failure after initiation of high-dose or multiple NSAIDs have been reported in HIV-infected patients with risk factors for renal dysfunction who appeared stable on TDF. Some patients required hospitalization and renal replacement therapy. Alternatives to NSAIDs should be considered, if needed, in patients at risk for renal dysfunction.

Persistent or worsening bone pain, pain in extremities, fractures, and/or muscular pain or weakness may be manifestations of proximal renal tubulopathy and should prompt an evaluation of renal function in at-risk patients.

Prior to initiation and during use of STRIBILD, on a clinically appropriate schedule, assess serum creatinine, estimated creatinine clearance, urine glucose, and urine protein in all patients. In patients with chronic kidney disease, also assess serum phosphorus. Discontinue STRIBILD in patients who develop clinically significant decreases in renal function or evidence of Fanconi syndrome. Initiation of STRIBILD in patients with estimated creatinine clearance below 70 mL per minute is not recommended [see Dosage and Administration (2.1)].

Although cobicistat (a component of STRIBILD) may cause modest increases in serum creatinine and modest declines in estimated creatinine clearance without affecting renal glomerular function [see Adverse Reactions (6.1)], patients who experience a confirmed increase in serum creatinine of greater than 0.4 mg per dL from baseline should be closely monitored for renal safety.

The emtricitabine and TDF components of STRIBILD are primarily excreted by the kidney. STRIBILD should be discontinued if estimated creatinine clearance declines below 50 mL per minute as dose interval adjustment required for emtricitabine and TDF cannot be achieved with the fixed-dose combination tablet [see Use in Specific Populations (8.6)].

5.3 Lactic Acidosis/Severe Hepatomegaly with Steatosis

Lactic acidosis and severe hepatomegaly with steatosis, including fatal cases, have been reported with the use of nucleoside analogs, including TDF and emtricitabine, components of STRIBILD, alone or in combination with other antiretrovirals. Treatment with STRIBILD should be suspended in any patient who develops clinical or laboratory findings suggestive of lactic acidosis or pronounced hepatotoxicity (which may include hepatomegaly and steatosis even in the absence of marked transaminase elevations).

5.4 Risk of Adverse Reactions or Loss of Virologic Response Due to Drug Interactions

The concomitant use of STRIBILD and other drugs may result in known or potentially significant drug interactions, some of which may lead to [see Contraindications (4) and Drug Interactions (7)]:

- Loss of therapeutic effect of STRIBILD and possible development of resistance.
- Clinically significant adverse reactions, potentially leading to severe, life-threatening, or fatal events, from greater exposures of concomitant drugs metabolized by CYP3A.
- Loss of therapeutic effect of concomitant drugs that utilize CYP3A to form active metabolites.

See Table 5 for steps to prevent or manage these possible and known significant drug interactions, including dosing recommendations [see Drug Interactions (7)]. Consider the potential for drug interactions prior to and during STRIBILD therapy; review concomitant medications during STRIBILD therapy; and monitor for the adverse reactions associated with the concomitant drugs.

5.5 Bone Loss and Mineralization Defects

Bone Mineral Density

In clinical trials in HIV-1 infected adults, TDF (a component of STRIBILD) was associated with slightly greater decreases in bone mineral density (BMD) and increases in biochemical markers of bone metabolism, suggesting increased bone turnover relative to comparators. Serum parathyroid hormone levels and 1,25 Vitamin D levels were also higher in subjects receiving TDF. For additional information, [see Adverse Reactions (6.1)] and consult the TDF prescribing information.

Clinical trials evaluating TDF in pediatric and adolescent subjects were conducted. Under normal circumstances, BMD increases rapidly in pediatric patients. In HIV-1 infected subjects aged 2 years to less than 18 years, bone effects were similar to those observed in adult subjects and suggest increased bone turnover. Total body BMD gain was less in the TDF-treated HIV-1 infected pediatric subjects as compared to the control groups. In all pediatric trials, skeletal growth (height) appeared to be unaffected. For more information, please consult the TDF prescribing information.

The effects of TDF-associated changes in BMD and biochemical markers on long-term bone health and future fracture risk are unknown. Assessment of BMD should be considered for HIV-1 infected adult and pediatric patients who have a history of pathologic bone fracture or other risk factors for osteoporosis or bone loss. Although the effect of supplementation with calcium and Vitamin D was not studied, such supplementation may be beneficial in all patients. If bone abnormalities are suspected, then appropriate consultation should be obtained.

Mineralization Defects

Cases of osteomalacia associated with proximal renal tubulopathy, manifested as bone pain or pain in extremities and which may contribute to fractures, have been reported in association with the use of TDF [see Adverse Reactions (6.2)]. Arthralgias and muscle pain or weakness have also been reported in cases of proximal renal tubulopathy. Hypophosphatemia and osteomalacia secondary to proximal renal tubulopathy should be considered in patients at risk of renal dysfunction who present with persistent or worsening bone or muscle symptoms while receiving products containing TDF [see Warnings and Precautions (5.2)].

5.6 Immune Reconstitution Syndrome

Immune reconstitution syndrome has been reported in patients treated with combination antiretroviral therapy, including STRIBILD. During the initial phase of combination antiretroviral treatment, patients whose immune system responds may develop an inflammatory response to indolent or residual opportunistic infections (such as Mycobacterium avium infection, cytomegalovirus, Pneumocystis jirovecii pneumonia (PCP), or tuberculosis), which may necessitate further evaluation and treatment.

Autoimmune disorders (such as Graves' disease, polymyositis, Guillain-Barré syndrome, and autoimmune hepatitis) have also been reported to occur in the setting of immune reconstitution; however, the time to onset is more variable and can occur many months after initiation of treatment.

6 ADVERSE REACTIONS

The following adverse reactions are discussed in other sections of the labeling:

- Severe Acute Exacerbations of Hepatitis B in Patients Coinfected with HIV-1 and HBV [see Warnings and Precautions (5.1)].
- New Onset or Worsening Renal Impairment [see Warnings and Precautions (5.2)].
- Lactic Acidosis/Severe Hepatomegaly with Steatosis [see Warnings and Precautions (5.3)].
- Bone Loss and Mineralization Defects [see Warnings and Precautions (5.5)].
- Immune Reconstitution Syndrome [see Warnings and Precautions (5.6)].

6.1 Clinical Trials Experience

Because clinical trials are conducted under widely varying conditions, adverse reaction rates observed in the clinical trials of a drug cannot be directly compared to rates in the clinical trials of another drug and may not reflect the rates observed in practice.

Clinical Trials in HIV-1 Infected Adult Subjects with No Antiretroviral Treatment History

The safety assessment of STRIBILD is based on the Week-144 pooled data from 1408 subjects in two randomized, double-blind, active-controlled clinical trials, Study 102 and Study 103, in antiretroviral treatment-naïve HIV-1 infected adult subjects [see Clinical Studies (14)]. A total of 701 subjects received STRIBILD once daily in these two studies.

The proportion of subjects who discontinued treatment with STRIBILD, ATRIPLA, or ATV+RTV+TRUVADA due to adverse events, regardless of severity, was 6.0%, 7.4%, and 8.5%, respectively. Table 1 displays the frequency of adverse reactions greater than or equal to 5% of subjects in any treatment arm.

Table 1 Adverse Reactions [Frequencies of adverse reactions are based on all treatment-emergent adverse events attributed to study drugs.] (All Grades) Reported in ≥5% of Adult Subjects in Any Treatment Arm in Studies 102 and 103 (Week-144 Analysis)
 | STRIBILD N=701 | ATRIPLA N=352 | ATV+RTV+TRUVADA N=355
EYE DISORDERS
Ocular icterus | <1% | 0% | 13%
GASTROINTESTINAL DISORDERS
Diarrhea | 12% | 11% | 17%
Flatulence | 2% | <1% | 8%
Nausea | 16% | 9% | 14%
GENERAL DISORDERS AND ADMINISTRATION SITE CONDITIONS
Fatigue | 4% | 8% | 6%
HEPATOBILIARY DISORDERS
Jaundice | 0% | <1% | 9%
NERVOUS SYSTEM DISORDERS
Somnolence | 1% | 7% | 1%
Headache | 7% | 4% | 6%
Dizziness | 3% | 21% | 5%
PSYCHIATRIC DISORDERS
Insomnia | 3% | 9% | 1%
Abnormal dreams | 9% | 27% | 4%
SKIN AND SUBCUTANEOUS TISSUE DISORDERS
Rash [Rash event includes dermatitis, drug eruption, eczema, pruritus, pruritus generalized, rash, rash erythematous, rash generalized, rash macular, rash maculo-papular, rash morbilliform, rash papular, rash pruritic, and urticaria.] | 4% | 15% | 6%

See Warnings and Precautions (5.2) for a discussion of renal adverse reactions from clinical trials experience with STRIBILD.

Additional adverse reactions observed with STRIBILD included suicidal ideation and suicide attempt (0.3%), all in subjects with a preexisting history of depression or psychiatric illness.

Clinical Trials in Virologically Suppressed HIV-1 Infected Adult Subjects

No new adverse reactions to STRIBILD through Week 48 were identified in 584 virologically stably suppressed adult subjects switching to STRIBILD from a regimen containing a RTV-boosted protease inhibitor (PI) or a non-nucleoside reverse transcriptase inhibitor (NNRTI). In a combined analysis of studies 115 and 121, the frequency of adverse reactions (all grades) was 24% in subjects switching to STRIBILD compared to 6% of subjects in either group who stayed on their baseline antiretroviral regimen, RTV-boosted PI+TRUVADA or NNRTI+TRUVADA. Common adverse reactions that occurred in greater than or equal to 2% of subjects switching to STRIBILD were nausea (4%), flatulence (2%), and headache (2%). The proportion of subjects who discontinued treatment with STRIBILD, the RTV-boosted PI, or the NNRTI due to adverse events was 2%, 3%, and 1%, respectively.

Clinical Trials of the Components of STRIBILD in Adult Subjects

Emtricitabine and TDF: In addition to the adverse reactions observed with STRIBILD, the following adverse reactions occurred in at least 5% of treatment-experienced or treatment-naïve subjects receiving emtricitabine or TDF with other antiretroviral agents in other clinical trials: depression, abdominal pain, dyspepsia, vomiting, fever, pain, nasopharyngitis, pneumonia, sinusitis, upper respiratory tract infection, arthralgia, back pain, myalgia, paresthesia, peripheral neuropathy (including peripheral neuritis and neuropathy), anxiety, increased cough, and rhinitis.

Skin discoloration has been reported with higher frequency among emtricitabine-treated subjects; it was manifested by hyperpigmentation on the palms and/or soles and was generally mild and asymptomatic. The mechanism and clinical significance are unknown.

Laboratory Abnormalities:

The frequency of laboratory abnormalities (Grades 3–4) occurring in at least 2% of subjects receiving STRIBILD in studies 102 and 103 are presented in Table 2.

Table 2 Laboratory Abnormalities (Grades 3–4) Reported in ≥2% of Adult Subjects Receiving STRIBILD in Studies 102 and 103 (Week-144 Analysis)
Laboratory Parameter Abnormality [Frequencies are based on treatment-emergent laboratory abnormalities.] , [For subjects with serum amylase >1.5 × upper limit of normal (ULN), lipase test was also performed. The frequency of increased lipase (Grades 3–4) occurring in STRIBILD (N=69), ATRIPLA (N=40), and ATV+RTV+TRUVADA (N=38) was 17%, 15%, and 24%, respectively.] | STRIBILD N=701 | ATRIPLA N=352 | ATV+RTV+TRUVADA N=355
AST (>5.0 × ULN) | 3% | 6% | 6%
ALT (>3.0 × ULN) | 2% | 5% | 4%
Amylase (>2.0 × ULN) | 3% | 3% | 5%
Creatine Kinase (≥10.0 × ULN) | 8% | 15% | 11%
Urine RBC (Hematuria) (>75 RBC/HPF) | 4% | 2% | 4%

In Study 103, BMD was assessed by DEXA in a nonrandom subset of 120 subjects (STRIBILD group, N=54; ATV+RTV+TRUVADA group, N=66). Mean percentage decreases in BMD from baseline to Week 144 in the STRIBILD group were comparable to that in the ATV+RTV+TRUVADA group at the lumbar spine (−1.43% versus −3.68%, respectively) and at the hip (−2.83% versus −3.77%, respectively). In studies 102 and 103, bone fractures occurred in 27 subjects (3.9%) in the STRIBILD group, 8 subjects (2.3%) in the ATRIPLA group, and 19 subjects (5.4%) in the ATV+RTV+TRUVADA group. These findings were consistent with data from an earlier 144-week trial of treatment-naïve subjects receiving TDF + lamivudine + efavirenz.

Proteinuria (all grades) occurred in 52% of subjects receiving STRIBILD, 41% of subjects receiving ATRIPLA, and 42% of subjects receiving ATV+RTV+TRUVADA.

The cobicistat component of STRIBILD has been shown to increase serum creatinine and decrease estimated creatinine clearance due to inhibition of tubular secretion of creatinine without affecting renal glomerular function. In studies 102 and 103, increases in serum creatinine and decreases in estimated creatinine clearance occurred early in treatment with STRIBILD, after which levels stabilized. Table 3 displays the mean changes in serum creatinine and eGFR levels at Week 144 and the percentage of subjects with elevations in serum creatinine (all grades).

Table 3 Change from Baseline in Serum Creatinine and eGFR and Incidence of Elevated Serum Creatinine (All Grades) in Studies 102 and 103 at Week 144
 | STRIBILD N=701 | ATRIPLA N=352 | ATV+RTV+TRUVADA N=355
Serum Creatinine (mg/dL) [Mean change ± standard deviation] | 0.14 (±0.14) | 0.01 (±0.12) | 0.09 (±0.15)
eGFR by Cockcroft-Gault (mL/minute) | −14.0 (±16.6) | −1.9 (±17.9) | −9.8 (±19.4)
Subjects with Elevations in Serum Creatinine (All Grades) (%) | 12 | 2 | 6

Emtricitabine or TDF: In addition to the laboratory abnormalities observed with STRIBILD, the following laboratory abnormalities have been previously reported in subjects treated with emtricitabine or TDF with other antiretroviral agents in other clinical trials: Grade 3 or 4 laboratory abnormalities of ALT (M: greater than 215 U per L; F: greater than 170 U per L), alkaline phosphatase (greater than 550 U per L), bilirubin (greater than 2.5 × ULN), serum glucose (less than 40 or greater than 250 mg per dL), glycosuria (greater than or equal to 3+), neutrophils (less than 750 per mm^3), fasting cholesterol (greater than 240 mg per dL), and fasting triglycerides (greater than 750 mg per dL).

Serum Lipids: In the clinical trials of STRIBILD, a similar percentage of subjects receiving STRIBILD, ATRIPLA, and ATV+RTV+TRUVADA were on lipid-lowering agents at baseline (12%, 12%, and 13%, respectively). While receiving study drug through Week 144, an additional 11% of STRIBILD subjects were started on lipid-lowering agents, compared to 13% of ATRIPLA and 12% of ATV+RTV+TRUVADA subjects.

Changes from baseline in total cholesterol, HDL-cholesterol, LDL-cholesterol, and triglycerides are presented in Table 4.

Table 4 Lipid Values, Mean Change from Baseline at Week 144 in Adult Subjects Receiving STRIBILD or Comparator in Studies 102 and 103
 | STRIBILD N=701 |  | ATRIPLA N=352 |  | ATV+RTV+TRUVADA N=355
 | Baseline | Week 144 | Baseline | Week 144 | Baseline | Week 144
 | mg/dL | Change [The change from baseline is the mean of within-patient changes from baseline for patients with both baseline and Week 144 values.] | mg/dL | Change | mg/dL | Change
Total Cholesterol (fasted) | 166 [N=675] | +17 [N=535] | 161 [N=343] | +22 [N=262] | 168 [N=337] | +16 [N=243]
HDL-cholesterol (fasted) | 43 [N=675] | +7 [N=535] | 43 [N=343] | +9 [N=262] | 42 [N=335] | +7 [N=242]
LDL-cholesterol (fasted) | 100 [N=675] | +15 [N=535] | 97 [N=343] | +19 [N=262] | 101 [N=337] | +18 [N=242]
Triglycerides (fasted) | 122 [N=675] | +12 [N=535] | 121 [N=343] | +5 [N=262] | 132 [N=337] | +22 [N=242]

Clinical Trials in Pediatric Subjects

The safety of STRIBILD in 50 HIV-1 infected, treatment-naïve pediatric subjects aged 12 to less than 18 years and weighing at least 35 kg was evaluated through 48 weeks in an open-label clinical trial (Study 112) [see Clinical Studies (14.4)]. In this study, the safety profile of STRIBILD was similar to that in adults. Twenty-two subjects (44%) had treatment-emergent proteinuria (Grades 1–2). One subject met laboratory criteria for proximal renal tubulopathy, evidenced by sustained proteinuria and normoglycemic glycosuria beginning at Week 32. The subject continued to receive STRIBILD and was ultimately lost to follow-up.

Among the 50 pediatric subjects receiving STRIBILD for 48 weeks, mean BMD increased from baseline to Week 48, +0.68% at the lumbar spine and +0.77% for total body less head. Mean changes from baseline BMD Z-scores (height-age adjusted) to Week 48 were −0.09 for lumbar spine and −0.12 for total body less head. At Week 48, 7 STRIBILD subjects had significant (greater than or equal to 4%) lumbar spine BMD loss and 2 had significant total body less head BMD loss.

6.2 Postmarketing Experience

The following adverse reactions have been identified during post-approval use of TDF. Because postmarketing reactions are reported voluntarily from a population of uncertain size, it is not always possible to reliably estimate their frequency or establish a causal relationship to drug exposure. No additional postmarketing adverse reactions specific for emtricitabine have been identified.

Immune System Disorders

allergic reaction, including angioedema

Metabolism and Nutrition Disorders

lactic acidosis, hypokalemia, hypophosphatemia

Respiratory, Thoracic, and Mediastinal Disorders

dyspnea

Gastrointestinal Disorders

pancreatitis, increased amylase, abdominal pain

Hepatobiliary Disorders

hepatic steatosis, hepatitis, increased liver enzymes (most commonly AST, ALT, gamma GT)

Skin and Subcutaneous Tissue Disorders

rash

Musculoskeletal and Connective Tissue Disorders

rhabdomyolysis, osteomalacia (manifested as bone pain and which may contribute to fractures), muscular weakness, myopathy

Renal and Urinary Disorders

acute renal failure, renal failure, acute tubular necrosis, Fanconi syndrome, proximal renal tubulopathy, interstitial nephritis (including acute cases), nephrogenic diabetes insipidus, renal insufficiency, increased creatinine, proteinuria, polyuria

General Disorders and Administration Site Conditions

asthenia

The following adverse reactions, listed under the body system headings above, may occur as a consequence of proximal renal tubulopathy: rhabdomyolysis, osteomalacia, hypokalemia, muscular weakness, myopathy, hypophosphatemia.

7 DRUG INTERACTIONS

7.1 Not Recommended with Other Antiretroviral Medications

STRIBILD is a complete regimen for the treatment of HIV-1 infection; therefore, STRIBILD should not be administered with other antiretroviral medications for treatment of HIV-1 infection. Complete information regarding potential drug-drug interactions with other antiretroviral medications is not provided [see Contraindications (4), Warnings and Precautions (5.4) and Clinical Pharmacology (12.3)].

7.2 Potential for STRIBILD to Affect Other Drugs

Cobicistat, a component of STRIBILD, is an inhibitor of CYP3A and CYP2D6 and an inhibitor of the following transporters: P-glycoprotein (P-gp), BCRP, OATP1B1, and OATP1B3. Thus, coadministration of STRIBILD with drugs that are primarily metabolized by CYP3A or CYP2D6, or are substrates of P-gp, BCRP, OATP1B1, or OATP1B3, may result in increased plasma concentrations of such drugs. Coadministration of STRIBILD with drugs that have active metabolite(s) formed by CYP3A may result in reduced plasma concentration of these active metabolite(s) (Table 5).

Elvitegravir is a modest inducer of CYP2C9 and may decrease the plasma concentrations of CYP2C9 substrates.

7.3 Potential for Other Drugs to Affect One or More Components of STRIBILD

Elvitegravir and cobicistat, components of STRIBILD, are metabolized by CYP3A. Cobicistat is also metabolized, to a minor extent, by CYP2D6.

Drugs that induce CYP3A activity are expected to increase the clearance of elvitegravir and cobicistat, resulting in decreased plasma concentration of cobicistat and elvitegravir, which may lead to loss of therapeutic effect of STRIBILD and development of resistance (Table 5).

Coadministration of STRIBILD with other drugs that inhibit CYP3A may decrease the clearance and increase the plasma concentration of cobicistat (Table 5).

7.4 Drugs Affecting Renal Function

Because emtricitabine and tenofovir, components of STRIBILD, are primarily excreted by the kidneys by a combination of glomerular filtration and active tubular secretion, coadministration of STRIBILD with drugs that reduce renal function or compete for active tubular secretion may increase concentrations of emtricitabine, tenofovir, and other renally eliminated drugs and this may increase the risk of adverse reactions. Some examples of drugs that are eliminated by active tubular secretion include, but are not limited to, acyclovir, cidofovir, ganciclovir, valacyclovir, valganciclovir, aminoglycosides (e.g., gentamicin), and high-dose or multiple NSAIDs [see Warnings and Precautions (5.2)].

7.5 Established and Other Potentially Significant Interactions

Table 5 provides a listing of established or potentially clinically significant drug interactions. The drug interactions described are based on studies conducted with either STRIBILD or the components of STRIBILD (elvitegravir, cobicistat, emtricitabine, and TDF) as individual agents and/or in combination, or are predicted drug interactions that may occur with STRIBILD [for magnitude of interaction see Clinical Pharmacology (12.3)]. The table includes potentially significant interactions but is not all inclusive [see Contraindications (4) and Clinical Pharmacology (12.3)].

Table 5 Established and Other Potentially Significant [This table is not all inclusive.] Drug Interactions: Alteration in Dose or Regimen May Be Recommended Based on Drug Interaction Studies or Predicted Interaction
Concomitant Drug Class: Drug Name | Effect on Concentration [↑=Increase, ↓=Decrease] | Clinical Comment
Alpha 1-adrenoreceptor antagonist: alfuzosin | ↑ alfuzosin | Coadministration with alfuzosin is contraindicated due to potential for serious and/or life-threatening reactions such as hypotension.
Antiarrhythmics: e.g., amiodarone bepridil digoxin [Indicates that a drug-drug interaction trial was conducted.] disopyramide flecainide systemic lidocaine mexiletine propafenone quinidine | ↑ antiarrhythmics ↑ digoxin | Therapeutic concentration monitoring, if available, is recommended for antiarrhythmics when coadministered with STRIBILD.
Antibacterials: clarithromycin | ↑ clarithromycin ↑ cobicistat | Patients with CLcr greater than or equal to 60 mL/minute: No dose adjustment of clarithromycin is required. Patients with CLcr between 50 mL/minute and 60 mL/minute: The dose of clarithromycin should be reduced by 50%.
Anticoagulants: Direct Oral Anticoagulants (DOACs) apixaban rivaroxaban betrixaban dabigatran edoxaban | ↑ apixaban | Due to potentially increased bleeding risk, dosing recommendations for coadministration with STRIBILD depends on the apixaban dose. Refer to apixaban dosing instructions for coadministration with strong CYP3A and P-gp inhibitors in apixaban prescribing information.
 | ↑ rivaroxaban | Coadministration of rivaroxaban with STRIBILD is not recommended because it may lead to an increased bleeding risk.
 | ↑ betrixaban ↑ dabigatran ↑ edoxaban | Due to potentially increased bleeding risk, dosing recommendations for coadministration of betrixaban, dabigatran, or edoxaban with a P-gp inhibitor such as STRIBILD depends on DOAC indication and renal function. Refer to DOAC dosing instructions for coadministration with P-gp inhibitors in DOAC prescribing information.
warfarin | Effect on warfarin unknown | Monitor international normalized ratio (INR) upon coadministration of warfarin with STRIBILD.
Anticonvulsants: carbamazepine phenobarbital phenytoin | ↓ elvitegravir ↓ cobicistat | Coadministration with carbamazepine, phenobarbital, or phenytoin is contraindicated due to potential for loss of elvitegravir therapeutic effect and development of resistance.
oxcarbazepine |  | Alternative anticonvulsants should be considered when STRIBILD is coadministered with oxcarbazepine.
clonazepam ethosuximide | ↑ clonazepam ↑ ethosuximide | Clinical monitoring is recommended upon coadministration of clonazepam or ethosuximide with STRIBILD.
Antidepressants: Selective Serotonin Reuptake Inhibitors (SSRIs) e.g., paroxetine | ↑ SSRIs (except sertraline) ↑ TCAs ↑ trazodone | Careful dose titration of the antidepressant and monitoring for antidepressant response are recommended when coadministered with STRIBILD.
Tricyclic Antidepressants (TCAs) e.g., amitriptyline desipramine imipramine nortriptyline bupropion
trazodone
Antifungals: itraconazole ketoconazole voriconazole | ↑ elvitegravir ↑ cobicistat ↑ itraconazole ↑ ketoconazole ↑ voriconazole | When coadministered with STRIBILD, the maximum daily dose of ketoconazole or itraconazole should not exceed 200 mg per day. An assessment of benefit/risk ratio is recommended to justify use of voriconazole with STRIBILD.
Anti-gout: colchicine | ↑ colchicine | STRIBILD is not recommended to be coadministered with colchicine to patients with renal or hepatic impairment. Treatment of gout-flares – coadministration of colchicine in patients receiving STRIBILD: 0.6 mg (1 tablet) × 1 dose, followed by 0.3 mg (half tablet) 1 hour later. Treatment course to be repeated no earlier than 3 days. Prophylaxis of gout-flares – coadministration of colchicine in patients receiving STRIBILD: If the original regimen was 0.6 mg twice a day, the regimen should be adjusted to 0.3 mg once a day. If the original regimen was 0.6 mg once a day, the regimen should be adjusted to 0.3 mg once every other day. Treatment of familial Mediterranean fever – coadministration of colchicine in patients receiving STRIBILD: Maximum daily dose of 0.6 mg (may be given as 0.3 mg twice a day).
Antimycobacterial: rifampin | ↓ elvitegravir ↓ cobicistat | Coadministration with rifampin is contraindicated due to potential for loss of elvitegravir therapeutic effect and development of resistance.
rifabutin rifapentine |  | Coadministration of STRIBILD with rifabutin or rifapentine is not recommended.
Antiplatelets:
ticagrelor clopidogrel | ↑ ticagrelor ↓ clopidogrel active metabolite | Coadministration with ticagrelor is not recommended. Coadministration with clopidogrel is not recommended due to potential reduction of the antiplatelet activity of clopidogrel.
Antipsychotics:
lurasidone | ↑ lurasidone | Coadministration with lurasidone is contraindicated due to potential for serious and/or life-threatening reactions.
pimozide | ↑ pimozide | Coadministration with pimozide is contraindicated due to potential for serious and/or life-threatening reactions such as cardiac arrhythmias.
quetiapine | ↑ quetiapine | Initiation of STRIBILD in patients taking quetiapine: Consider alternative antiretroviral therapy to avoid increases in quetiapine exposure. If coadministration is necessary, reduce the quetiapine dose to 1/6 of the current dose and monitor for quetiapine-associated adverse reactions. Refer to the quetiapine prescribing information for recommendations on adverse reaction monitoring. Initiation of quetiapine in patients taking STRIBILD: Refer to the quetiapine prescribing information for initial dosing and titration of quetiapine.
Other antipsychotics e.g., perphenazine risperidone thioridazine | ↑ antipsychotic | A decrease in the dose of antipsychotics that are metabolized by CYP3A4 or CYP2D6 may be needed when coadministered with STRIBILD.
Beta-Blockers: e.g., metoprolol timolol | ↑ beta-blockers | Clinical monitoring is recommended and a dose decrease of the beta-blocker may be necessary when these agents are coadministered with STRIBILD.
Calcium Channel Blockers: e.g., amlodipine diltiazem felodipine nicardipine nifedipine verapamil | ↑ calcium channel blockers | Clinical monitoring is recommended upon coadministration of calcium channel blockers with STRIBILD.
Corticosteroids: e.g., betamethasone budesonide ciclesonide dexamethasone fluticasone methylprednisolone mometasone triamcinolone | ↓ elvitegravir ↓ cobicistat ↑ corticosteroids | Coadministration with oral dexamethasone or other systemic corticosteroids that induce CYP3A may result in loss of therapeutic effect and development of resistance to elvitegravir. Consider alternative corticosteroids. Coadministration with corticosteroids (all routes of administration) whose exposures are significantly increased by strong CYP3A inhibitors can increase the risk for Cushing's syndrome and adrenal suppression. Alternative corticosteroids including beclomethasone, prednisone, and prednisolone (whose PK and/or PD are less affected by strong CYP3A inhibitors relative to other studied steroids) should be considered, particularly for long-term use.
Endothelin Receptor Antagonists: bosentan | ↑ bosentan | Coadministration of bosentan in patients on STRIBILD: In patients who have been receiving STRIBILD for at least 10 days, start bosentan at 62.5 mg once daily or every other day based upon individual tolerability. Coadministration of STRIBILD in patients on bosentan: Discontinue use of bosentan at least 36 hours prior to initiation of STRIBILD. After at least 10 days following the initiation of STRIBILD, resume bosentan at 62.5 mg once daily or every other day based upon individual tolerability.
Ergot Derivatives: dihydroergotamine, ergotamine, methylergonovine | ↑ ergot derivatives | Coadministration is contraindicated due to potential for serious and/or life-threatening reactions such as acute ergot toxicity characterized by peripheral vasospasm and ischemia of the extremities and other tissues.
Hepatitis C Antiviral Agents: ledipasvir/sofosbuvir sofosbuvir/velpatasvir sofosbuvir/velpatasvir/voxilaprevir | ↑ tenofovir | The safety of increased tenofovir concentrations in the setting of HARVONI® (ledipasvir/sofosbuvir) and STRIBILD has not been established. Coadministration is not recommended. Patients receiving STRIBILD concomitantly with EPCLUSA® (sofosbuvir/velpatasvir) or VOSEVI® (sofosbuvir/velpatasvir/voxilaprevir) should be monitored for adverse reactions associated with tenofovir disoproxil fumarate.
Herbal Products: St. John's wort (Hypericum perforatum) | ↓ elvitegravir ↓ cobicistat | Coadministration is contraindicated due to potential for loss of elvitegravir therapeutic effect and development of resistance.
Hormonal Contraceptives: drospirenone/ethinyl estradiol levonorgestrel norgestimate/ethinyl estradiol | ↑ drospirenone ↑ levonorgestrel ↑ norgestimate ↓ ethinyl estradiol | Additional or alternative non-hormonal forms of contraception should be considered when estrogen based contraceptives are coadministered with STRIBILD. Plasma concentrations of drospirenone may be increased when coadministered with cobicistat- containing products. Clinical monitoring is recommended due to the potential for hyperkalemia. The effects of increases in the concentration of the progestational component norgestimate are not fully known and can include increased risk of insulin resistance, dyslipidemia, acne, and venous thrombosis. The potential risks and benefits associated with coadministration of norgestimate/ethinyl estradiol with STRIBILD should be considered, particularly in women who have risk factors for these events. Coadministration of STRIBILD with other hormonal contraceptives (e.g., contraceptive patch, contraceptive vaginal ring, or injectable contraceptives) or oral contraceptives containing progestogens other than drospirenone, levonorgestrel, or norgestimate has not been studied; therefore, alternative (non-hormonal) methods of contraception can be considered.
Immuno-suppressants: e.g., cyclosporine sirolimus tacrolimus | ↑ immuno-suppressants | Therapeutic monitoring of the immunosuppressive agents is recommended upon coadministration with STRIBILD.
Lipid-modifying Agents: HMG-CoA Reductase Inhibitors:
lovastatin simvastatin | ↑ lovastatin ↑ simvastatin | Coadministration with lovastatin or simvastatin is contraindicated due to potential for serious reactions such as myopathy including rhabdomyolysis.
atorvastatin | ↑ atorvastatin | Initiate atorvastatin with the lowest starting dose of atorvastatin and titrate carefully while monitoring for safety (e.g., myopathy). Do not exceed a dosage of atorvastatin 20 mg daily.
Other Lipid-modifying Agents: lomitapide | ↑ lomitapide | Coadministration with lomitapide is contraindicated due to potential for markedly increased transaminases.
Narcotic Analgesics: buprenorphine/naloxone | ↑ buprenorphine ↑ norbuprenorphine ↓ naloxone | Patients should be closely monitored for sedation and cognitive effects.
fentanyl | ↑ fentanyl | Careful monitoring of therapeutic and adverse effects of fentanyl (including potentially fatal respiratory depression) is recommended with coadministration.
tramadol | ↑ tramadol | A dose decrease may be needed for tramadol with concomitant use.
Inhaled Beta Agonist: salmeterol | ↑ salmeterol | Coadministration of salmeterol and STRIBILD is not recommended because it may result in increased risk of cardiovascular adverse events associated with salmeterol, including QT prolongation, palpitations, and sinus tachycardia.
Medications or Oral Supplements Containing Polyvalent Cations (e.g., Mg, Al, Ca, Fe, Zn): calcium or iron supplements, including multivitamins cation-containing antacids or laxatives sucralfate buffered medications | ↓ elvitegravir | Separate STRIBILD and administration of medications, antacids, or oral supplements containing polyvalent cations by at least 2 hours.
Phosphodiesterase-5 (PDE-5) Inhibitors: sildenafil tadalafil vardenafil | ↑ PDE-5 inhibitors | Coadministration of sildenafil with STRIBILD is contraindicated when used for treatment of pulmonary arterial hypertension (PAH), due to potential for PDE-5 inhibitor associated adverse reactions, including hypotension, syncope, visual disturbances, and priapism. Use of tadalafil for PAH:; - Coadministration of tadalafil in patients on STRIBILD: In patients receiving STRIBILD for at least 1 week, start tadalafil at 20 mg once daily. Increase tadalafil dose to 40 mg once daily based upon individual tolerability. - Coadministration of STRIBILD in patients on tadalafil: Avoid use of tadalafil during the initiation of STRIBILD. Stop tadalafil at least 24 hours prior to starting STRIBILD. After at least one week following initiation of STRIBILD, resume tadalafil at 20 mg once daily. Increase tadalafil dose to 40 mg once daily based upon individual tolerability.; Use of PDE-5 inhibitors for erectile dysfunction: The below PDE-5 inhibitors can be used along with increased monitoring for PDE-5-inhibitor associated adverse events:; - Sildenafil at a single dose not exceeding 25 mg in 48 hours, or - Tadalafil at a single dose not exceeding 10 mg in 72 hours, or - Vardenafil at a single dose not exceeding 2.5 mg in 72 hours
Sedative/hypnotics:
midazolam (oral), triazolam | ↑ midazolam ↑ triazolam | Coadministration with triazolam or orally administered midazolam is contraindicated due to potential for serious and/or life-threatening reactions such as prolonged or increased sedation or respiratory depression. Triazolam and orally administered midazolam are extensively metabolized by CYP3A. Coadministration of triazolam or orally administered midazolam with STRIBILD may cause large increases in the concentrations of these benzodiazepines.
Other benzodiazepines: e.g., parenterally administered midazolam clorazepate diazepam estazolam flurazepam buspirone zolpidem | ↑ sedatives/hypnotics | Coadministration of parenteral midazolam with STRIBILD should be done in a setting that ensures close clinical monitoring and appropriate medical management in case of respiratory depression and/or prolonged sedation. Dosage reduction for midazolam should be considered, especially if more than a single dose of midazolam is administered. With other sedative/hypnotics, dose reduction may be necessary and clinical monitoring is recommended.

7.6 Drugs without Clinically Significant Interactions with STRIBILD

Based on drug interaction studies conducted with the components of STRIBILD, no clinically significant drug interactions have been observed or are expected when STRIBILD is combined with the following drugs: famciclovir, famotidine, methadone, omeprazole, prasugrel (active metabolite), and sertraline.

8 USE IN SPECIFIC POPULATIONS

8.1 Pregnancy

Pregnancy Exposure Registry

There is a pregnancy exposure registry that monitors pregnancy outcomes in women exposed to STRIBILD during pregnancy. Healthcare providers are encouraged to register patients by calling the Antiretroviral Pregnancy Registry (APR) at 1-800-258-4263.

Risk Summary

STRIBILD is not recommended during pregnancy [see Dosage and Administration (2.5)]. A literature report evaluating the pharmacokinetics (PK) of antiretrovirals during pregnancy demonstrated substantially lower exposures of elvitegravir and cobicistat in the second and third trimesters (see Data).

Prospective pregnancy data from the APR are not sufficient to adequately assess the risk of birth defects or miscarriage. However, elvitegravir, cobicistat, emtricitabine, and TDF use during pregnancy have been evaluated in a limited number of individuals as reported to the APR. Available data from the APR show no significant difference in the overall risk of major birth defects for elvitegravir, cobicistat, emtricitabine, or TDF compared with the background rate for major birth defects of 2.7% in a U.S. reference population of the Metropolitan Atlanta Congenital Defects Program (MACDP) (see Data). The rate of miscarriage is not reported in the APR. In the U.S. general population, the estimated background risk of miscarriage in clinically recognized pregnancies is 15–20%.

In animal studies, no adverse developmental effects were observed when the components of STRIBILD were administered separately during the period of organogenesis at exposures up to 23 and 0.2 times (rats and rabbits, respectively, elvitegravir), 1.8 and 4.3 times (rats and rabbits, respectively, cobicistat), and 60 and 120 times (mice and rabbits, respectively, emtricitabine) the exposure at the recommended daily dose of these components in STRIBILD, and at 14 and 19 times (rats and rabbits, respectively, TDF) the human dose based on body surface area comparisons [see Data]. Likewise, no adverse developmental effects were seen when elvitegravir or cobicistat was administered to rats through lactation at exposures up to 18 times or 1.2 times, respectively, the exposure at the recommended daily therapeutic dose, and when emtricitabine was administered to mice through lactation at exposures up to approximately 60 times the exposure at the recommended daily therapeutic dose. No adverse effects were observed in the offspring of rats when TDF was administered through lactation at tenofovir exposures of approximately 2.7 times the exposure at the recommended daily dosage of STRIBILD.

Data

Human Data

A prospective study, reported in the literature, enrolled 30 pregnant women living with HIV who were receiving elvitegravir and cobicistat-based regimens in the second or third trimesters of pregnancy and through 6 to 12 weeks postpartum to evaluate the pharmacokinetics (PK) of antiretrovirals during pregnancy. Twenty-eight women completed the study through the postpartum period. Paired pregnancy/postpartum PK data were available from 14 and 24 women for the second and third trimesters, respectively. Exposures of elvitegravir and cobicistat were substantially lower during the second and third trimesters compared to postpartum. The proportion of pregnant women who were virologically suppressed was 77% in the second trimester, 92% in the third trimester, and 76% postpartum. No correlation was observed between viral suppression and elvitegravir exposure. HIV status was also assessed for infants: 25 were uninfected, 2 had indeterminate status, and no information was available for 3 infants.

Prospective reports from the APR of overall major birth defects in pregnancies exposed to the components of STRIBILD are compared with a U.S. background major birth defect rate. Methodological limitations of the APR include the use of MACDP as the external comparator group. The MACDP population is not disease-specific, evaluates women and infants from a limited geographic area, and does not include outcomes for births that occurred at <20 weeks gestation.

Elvitegravir: Based on prospective reports to the APR of exposures to elvitegravir-containing regimens during pregnancy resulting in live births (including over 300 exposed in the first trimester and over 60 exposed in the second/third trimester), the prevalence of birth defects in live births was 3.4% (95% CI: 1.7% to 6.0%) and 1.5% (95% CI: 0% to 7.9%) following first and second/third trimester exposure, respectively, to elvitegravir-containing regimens.

Cobicistat: Based on prospective reports to the APR of exposures to cobicistat-containing regimens during pregnancy resulting in live births (including over 400 exposed in the first trimester and over 80 exposed in the second/third trimester), the prevalence of birth defects in live births was 3.9% (95% CI: 2.2% to 6.3%) and 1.2% (95% CI: 0.0% to 6.5%) following first and second/third trimester exposure, respectively, to cobicistat-containing regimens.

Emtricitabine: Based on prospective reports to the APR of exposures to emtricitabine-containing regimens during pregnancy resulting in live births (including over 3,600 exposed in the first trimester and over 1,400 exposed in the second/third trimester), the prevalence of birth defects in live births was 2.6% (95% CI: 2.1% to 3.2%) and 2.4% (95% CI: 1.6% to 3.3%) following first and second/third trimester exposure, respectively, to emtricitabine-containing regimens.

Tenofovir DF: Based on prospective reports to the APR of exposures to TDF-containing regimens during pregnancy resulting in live births (including over 4,200 exposed in the first trimester and over 1,800 exposed in the second/third trimester), the prevalence of birth defects in live births was 2.4% (95% CI: 1.9% to 2.9%) and 2.4% (95% CI: 1.8% to 3.2%) following first and second/third trimester exposure, respectively, to TDF-containing regimens.

Animal Data

Elvitegravir: Elvitegravir was administered orally to pregnant rats (at 0, 300, 1000, and 2000 mg/kg/day), and rabbits (at 0, 50, 150, and 450 mg/kg/day) through organogenesis (on gestation days 7 through 17 and days 7 through 19, respectively). No significant toxicological effects were observed in embryo-fetal toxicity studies performed with elvitegravir in rats at exposures (AUC) approximately 23 times higher and in rabbits at approximately 0.2 times higher than human exposures at the recommended daily dose. In a pre- and postnatal developmental study in rats, elvitegravir was administered orally at doses of 0, 300, 1000, and 2000 mg/kg from gestation day 7 to day 20 of lactation. At doses of 2000 mg/kg/day of elvitegravir, neither maternal nor developmental toxicity was noted. Systemic exposures (AUC) at this dose were 18 times the human exposures at the recommended daily dose.

Cobicistat: Cobicistat was administered orally to pregnant rats at doses of 0, 25, 50, and 125 mg/kg/day on gestation day 6 to 17. Increases in post-implantation loss and decreased fetal weights were observed at a maternal toxic dose of 125 mg/kg/day. No malformations were noted at doses up to 125 mg/kg/day. Systemic exposures (AUC) at 50 mg/kg/day in pregnant females were 1.8 times higher than human exposures at the recommended daily dose.

In pregnant rabbits, cobicistat was administered orally at doses of 0, 20, 50, and 100 mg/kg/day during the gestation days 7 to 20. No maternal or embryo/fetal effects were noted at the highest dose of 100 mg/kg/day. Systemic exposures (AUC) at 100 mg/kg/day were 4.3 times higher than human exposures at the recommended daily dose. In a pre- and postnatal developmental study in rats, cobicistat was administered orally at doses of 0, 10, 30, and 75 mg/kg from gestation day 6 to postnatal day 20, 21, or 22. At doses of 75 mg/kg/day of cobicistat, neither maternal nor developmental toxicity was noted. Systemic exposures (AUC) at this dose were 1.2 times the human exposures at the recommended daily dose.

Emtricitabine: Emtricitabine was administered orally to pregnant mice (at 0, 250, 500, or 1000 mg/kg/day), and rabbits (at 0, 100, 300, or 1000 mg/kg/day) through organogenesis (on gestation days 6 through 15, and 7 through 19, respectively). No significant toxicological effects were observed in embryo-fetal toxicity studies performed with emtricitabine in mice at exposures (AUC) approximately 60 times higher and in rabbits at approximately 120 times higher than human exposures at the recommended daily dose. In a pre/postnatal development study in mice, emtricitabine was administered orally at doses up to 1000 mg/kg/day; no significant adverse effects directly related to drug were observed in the offspring exposed daily from before birth (in utero) through sexual maturity at daily exposures (AUC) of approximately 60 times higher than human exposures at the recommended daily dose.

Tenofovir DF: Tenofovir DF was administered orally to pregnant rats (at 0, 50, 150, or 450 mg/kg/day) and rabbits (at 0, 30, 100, or 300 mg/kg/day) through organogenesis (on gestation days 7 through 17, and 6 through 18, respectively). No significant toxicological effects were observed in embryo-fetal toxicity studies performed with TDF in rats at doses up to 14 times the human dose based on body surface area comparisons and in rabbits at doses up to 19 times the human dose based on body surface area comparisons. In a pre/postnatal development study in rats, TDF was administered orally through lactation at doses up to 600 mg/kg/day; no adverse effects were observed in the offspring at tenofovir exposures of approximately 2.7 times higher than human exposures at the recommended daily dose of STRIBILD.

8.2 Lactation

Risk Summary

The Centers for Disease Control and Prevention recommend that HIV-infected mothers not breastfeed their infants to avoid risking postnatal transmission of HIV.

Based on limited published data, emtricitabine and tenofovir have been shown to be present in human breast milk. It is not known whether elvitegravir or cobicistat are present in human breast milk, while elvitegravir and cobicistat have been shown to be present in rat milk (see Data).

It is not known if the components of STRIBILD affect milk production or have effects on the breastfed child. Because of the potential for: (1) HIV transmission (in HIV-negative infants); (2) developing viral resistance (in HIV-positive infants); and (3) adverse reactions in a breastfed infant similar to those seen in adults, instruct mothers not to breastfeed if they are receiving STRIBILD (see Data).

Animal Data

Elvitegravir: During the prenatal and postnatal developmental toxicology study at doses up to 2000 mg/kg/day mean elvitegravir milk to plasma ratio of 0.1 was measured 30 minutes after administration to rats on lactation day 14.

Cobicistat: During the prenatal and postnatal developmental toxicology study at doses up to 75 mg/kg/day mean cobicistat milk to plasma ratio of up to 1.9 was measured 2 hours after administration to rats on lactation day 10.

8.4 Pediatric Use

The pharmacokinetics, safety, and virologic and immunologic responses were evaluated in 50 treatment-naïve, HIV-1 infected subjects aged 12 to less than 18 years weighing at least 35 kg receiving STRIBILD through 48 weeks in an open-label trial (Study 112). The safety and efficacy of STRIBILD in these subjects was similar to that in antiretroviral treatment-naïve adults [see Dosage and Administration (2.2), Adverse Reactions (6.1), Clinical Pharmacology (12.3), and Clinical Studies (14.4)].

Safety and effectiveness of STRIBILD in pediatric patients less than 12 years of age or weighing less than 35 kg have not been established.

8.5 Geriatric Use

Clinical studies of STRIBILD did not include sufficient numbers of subjects aged 65 and over to determine whether they respond differently from younger subjects. In general, caution should be exercised in the administration of STRIBILD in elderly patients, keeping in mind the greater frequency of decreased hepatic, renal, or cardiac function, and of concomitant disease or other drug therapy [see Clinical Pharmacology (12.3)].

8.6 Renal Impairment

Initiation of STRIBILD in patients with estimated creatinine clearance below 70 mL per min is not recommended. Because STRIBILD is a fixed-dose combination tablet, STRIBILD should be discontinued if estimated creatinine clearance declines below 50 mL per minute during treatment with STRIBILD as dose interval adjustment required for emtricitabine and TDF cannot be achieved [see Warnings and Precautions (5.2), Adverse Reactions (6.1), Clinical Pharmacology (12.3), and Clinical Studies (14)].

No data are available to make dose recommendations for pediatric patients with renal impairment.

Clinical Trials in Adult Subjects with Mild to Moderate Renal Impairment

In Study 118, 33 HIV-1 infected treatment-naïve subjects with mild to moderate renal impairment (eGFR by Cockcroft-Gault method between 50 and 89 mL/minute) were studied in an open-label clinical trial evaluating the safety of 48 weeks of treatment with STRIBILD. After 48 weeks of treatment, the mean change in serum creatinine was 0.17 ± 0.14 mg/dL and the mean change in eGFR by Cockcroft-Gault method was −6.9 ± 9.0 mL/minute for subjects treated with STRIBILD.

Twelve of the 33 subjects studied had baseline eGFR between 50 and 70 mL/minute. Three subjects, all with baseline eGFR between 50–60 mL/minute, discontinued STRIBILD due to a renal adverse event. The safety of STRIBILD among 21 of the 33 subjects with baseline eGFR greater than or equal to 70 mL/minute was consistent with the safety profile in studies 102 and 103.

8.7 Hepatic Impairment

No dose adjustment of STRIBILD is required in patients with mild (Child-Pugh Class A) or moderate (Child-Pugh Class B) hepatic impairment. No pharmacokinetic or safety data are available regarding the use of STRIBILD in patients with severe hepatic impairment (Child-Pugh Class C). Therefore, STRIBILD is not recommended for use in patients with severe hepatic impairment [see Dosage and Administration (2.4) and Clinical Pharmacology (12.3)].

10 OVERDOSAGE

No data are available on overdose of STRIBILD in patients. If overdose occurs the patient must be monitored for evidence of toxicity. Treatment of overdose with STRIBILD consists of general supportive measures, including monitoring of vital signs as well as observation of the clinical status of the patient.

Elvitegravir: Limited clinical experience is available at doses higher than the therapeutic dose of elvitegravir. In one study, boosted elvitegravir equivalent to 2 times the therapeutic dose of 150 mg once daily for 10 days was administered to 42 healthy subjects. No severe adverse reactions were reported. The effects of higher doses are not known. As elvitegravir is highly bound to plasma proteins, it is unlikely that it will be significantly removed by hemodialysis or peritoneal dialysis.

Cobicistat: Limited clinical experience is available at doses higher than the therapeutic dose of cobicistat. In two studies, a single dose of cobicistat 400 mg (2.7 times the dose in STRIBILD) was administered to a total of 60 healthy subjects. No severe adverse reactions were reported. The effects of higher doses are not known. As cobicistat is highly bound to plasma proteins, it is unlikely that it will be significantly removed by hemodialysis or peritoneal dialysis.

Emtricitabine: Limited clinical experience is available at doses higher than the therapeutic dose of EMTRIVA®. In one clinical pharmacology study, single doses of emtricitabine 1200 mg (6 times the dose in STRIBILD) were administered to 11 subjects. No severe adverse reactions were reported. The effects of higher doses are not known.

Hemodialysis treatment removes approximately 30% of the emtricitabine dose over a 3-hour dialysis period starting within 1.5 hours of emtricitabine dosing (blood flow rate of 400 mL per minute and a dialysate flow rate of 600 mL per minute). It is not known whether emtricitabine can be removed by peritoneal dialysis.

Tenofovir DF: Limited clinical experience at doses higher than the therapeutic dose of VIREAD® 300 mg is available. In one study, 600 mg TDF (2 times the dosage in STRIBILD) was administered to 8 subjects orally for 28 days and no severe adverse reactions were reported. The effects of higher doses are not known. Tenofovir is efficiently removed by hemodialysis with an extraction coefficient of approximately 54%. Following a single 300 mg dose of VIREAD, a 4-hour hemodialysis session removed approximately 10% of the administered tenofovir dose.

11 DESCRIPTION

STRIBILD is a fixed-dose combination tablet containing elvitegravir, cobicistat, emtricitabine, and TDF for oral administration.

- Elvitegravir is an HIV-1 integrase strand transfer inhibitor.
- Cobicistat is a mechanism-based inhibitor of cytochrome P450 (CYP) enzymes of the CYP3A family.
- Emtricitabine is a synthetic nucleoside analog of cytidine. EMTRIVA is the brand name for emtricitabine.
- Tenofovir DF is converted in vivo to tenofovir, an acyclic nucleoside phosphonate (nucleotide) analog of adenosine 5'-monophosphate. VIREAD is the brand name for TDF.

Each tablet contains 150 mg of elvitegravir, 150 mg of cobicistat, 200 mg of emtricitabine, and 300 mg of TDF (equivalent to 245 mg of tenofovir disoproxil). The tablets include the following inactive ingredients: lactose monohydrate, microcrystalline cellulose, silicon dioxide, croscarmellose sodium, hydroxypropyl cellulose, sodium lauryl sulfate, and magnesium stearate. The tablets are film coated with a coating material containing indigo carmine (FD&C Blue #2) aluminum lake, polyethylene glycol, polyvinyl alcohol, talc, titanium dioxide, and yellow iron oxide.

Elvitegravir: The chemical name of elvitegravir is 6-(3-Chloro-2-fluorobenzyl)-1-[(2S)-1-hydroxy-3-methylbutan-2-yl]-7-methoxy-4-oxo-1,4-dihydroquinoline-3-carboxylic acid.

It has a molecular formula of C23H23ClFNO5 and a molecular weight of 447.9. It has the following structural formula:

Elvitegravir is a white to pale-yellow powder with a solubility of less than 0.3 micrograms per mL in water at 20 °C.

Cobicistat: The chemical name for cobicistat is 1,3-thiazol-5-ylmethyl [(2R,5R)-5-{[(2S)-2-[(methyl{[2-(propan-2-yl)-1,3-thiazol-4-yl]methyl}carbamoyl)amino]-4-(morpholin-4-yl)butanoyl]amino}-1,6-diphenylhexan-2-yl]carbamate.

It has a molecular formula of C40H53N7O5S2 and a molecular weight of 776.0. It has the following structural formula:

Cobicistat is adsorbed onto silicon dioxide. Cobicistat on silicon dioxide is a white to pale-yellow solid with a solubility of 0.1 mg per mL in water at 20 °C.

Emtricitabine: The chemical name of emtricitabine is 5-fluoro-1-[(2R,5S)-2-(hydroxymethyl)-1,3-oxathiolan-5-yl]cytosine. Emtricitabine is the (-)enantiomer of a thio analog of cytidine, which differs from other cytidine analogs in that it has a fluorine in the 5-position.

It has a molecular formula of C8H10FN3O3S and a molecular weight of 247.25. It has the following structural formula:

Emtricitabine is a white to off-white crystalline powder with a solubility of approximately 112 mg per mL in water at 25 °C.

Tenofovir DF: Tenofovir DF is a fumaric acid salt of the bis-isopropoxycarbonyloxymethyl ester derivative of tenofovir. The chemical name of TDF is 9-[(R)-2-[[bis[[(isopropoxycarbonyl)oxy]-methoxy]phosphinyl]methoxy]propyl]adenine fumarate (1:1). It has a molecular formula of C19H30N5O10P ∙ C4H4O4 and a molecular weight of 635.51. It has the following structural formula:

Tenofovir DF is a white to off-white crystalline powder with a solubility of 13.4 mg per mL in water at 25 °C. All dosages are expressed in terms of TDF except where otherwise noted.

12 CLINICAL PHARMACOLOGY

12.1 Mechanism of Action

STRIBILD is a fixed-dose combination of antiretroviral drugs elvitegravir (boosted by the CYP3A inhibitor cobicistat), emtricitabine, and TDF [see Microbiology (12.4)].

12.2 Pharmacodynamics

Effects on Electrocardiogram

Thorough QT studies have been conducted for elvitegravir and cobicistat. The effect of the other two components, tenofovir and emtricitabine, or the combination regimen STRIBILD on the QT interval is not known.

Elvitegravir: In a thorough QT/QTc study in 126 healthy subjects, elvitegravir (coadministered with 100 mg ritonavir) 125 mg and 250 mg (0.83 and 1.67 times the dose in STRIBILD) did not affect the QT/QTc interval and did not prolong the PR interval.

Cobicistat: In a thorough QT/QTc study in 48 healthy subjects, a single dose of cobicistat 250 mg and 400 mg (1.67 and 2.67 times the dose in STRIBILD) did not affect the QT/QTc interval. Prolongation of the PR interval was noted in subjects receiving cobicistat. The maximum mean (95% upper confidence bound) difference in PR from placebo after baseline-correction was 9.5 (12.1) msec for the 250 mg cobicistat dose and 20.2 (22.8) for the 400 mg cobicistat dose. Because the 150 mg cobicistat dose used in the STRIBILD fixed-dose combination tablet is lower than the lowest dose studied in the thorough QT study, it is unlikely that treatment with STRIBILD will result in clinically relevant PR prolongation.

Effects on Serum Creatinine

The effect of cobicistat on serum creatinine was investigated in a Phase 1 study in subjects with an eGFR of at least 80 mL per minute (N=18) and with an eGFR of 50 to 79 mL per minute (N=12). A statistically significant change of eGFRCG from baseline was observed after 7 days of treatment with cobicistat 150 mg among subjects with an eGFR of at least 80 mL per minute (−9.9 ± 13.1 mL/min) and subjects with an eGFR of 50 to 79 mL per minute (−11.9 ± 7.0 mL per minute). These decreases in eGFRCG were reversible after cobicistat was discontinued. The actual glomerular filtration rate, as determined by the clearance of probe drug iohexol, was not altered from baseline following treatment of cobicistat among subjects with an eGFR of at least 50 mL per minute, indicating cobicistat inhibits tubular secretion of creatinine, reflected as a reduction in eGFRCG, without affecting the actual glomerular filtration rate.

12.3 Pharmacokinetics

The pharmacokinetic properties of the components of STRIBILD are provided in Table 6. The multiple dose pharmacokinetic parameters of elvitegravir, cobicistat, emtricitabine, and tenofovir are provided in Table 7.

Table 6 Pharmacokinetic Properties of the Components of STRIBILD
 | Elvitegravir | Cobicistat | Emtricitabine | Tenofovir
Absorption
Tmax (h) | 4 | 3 | 3 | 2
Effect of light meal (relative to fasting) [Values refer to mean systemic exposure (90% confidence interval). STRIBILD light meal=~373 kcal, 20% fat; STRIBILD high fat meal=~800 kcal, 50% fat. Increase = ↑; Decrease = ↓] | ↑34% (↑19, ↑51) | ↑3% (↓10, ↑17) | ↓5% (↓9, 0) | ↑24% (↑18, ↑30)
Effect of high fat meal (relative to fasting) | ↑87% (↑66, ↑110) | ↓17% (↓27, ↓5) | ↓4% (↓8, 0) | ↑23% (↑17, ↑29)
Distribution
% Bound to human plasma proteins | ~99 | ~98 | <4 | <0.7
Source of protein binding data | Ex vivo | In vitro | In vitro | In vitro
Blood-to-plasma ratio | 0.73 | 0.5 | 0.6 | NC
Metabolism
Metabolism | CYP3A (major) UGT1A1/3 (minor) | CYP3A (major) CYP2D6 (minor) | Not significantly metabolized
Elimination
Major route of elimination | Metabolism |  | Glomerular filtration and active tubular secretion
T1/2 (h) [t1/2 values refer to median terminal plasma half-life.] | 12.9 | 3.5 | 10 | 12–18
% Of dose excreted in urine [Dosing in mass balance studies: elvitegravir (single dose administration of [^14C] elvitegravir, coadministered with 100 mg RTV); cobicistat (single-dose administration of [^14C] cobicistat after multiple dosing of cobicistat for six days); emtricitabine (single dose administration of [^14C] emtricitabine after multiple dosing of emtricitabine for ten days); mass balance study not conducted for tenofovir.] | 6.7 | 8.2 | 70 | 70–80
% Of dose excreted in feces | 94.8 | 86.2 | 13.7 | NC
NC=Not Calculated

Table 7 Pharmacokinetic Parameters of Elvitegravir, Cobicistat, Emtricitabine, and Tenofovir Exposure Following Oral Administration of STRIBILD in HIV-Infected Subjects
Parameter Mean ± SD [range, min:max] | Elvitegravir [From Population Pharmacokinetic analysis, N=419.] | Cobicistat [From Intensive Pharmacokinetic analysis, N=61–62, except cobicistat Ctrough N=53.] | Emtricitabine | Tenofovir
Cmax (microgram per mL) | 1.7 ± 0.4 [0.4:3.7] | 1.1 ± 0.4 [0.1:2.1] | 1.9 ± 0.5 [0.6:3.6] | 0.45 ± 0.2 [0.2:1.2]
AUCtau (microgram∙hour per mL) | 23.0 ± 7.5 [4.4:69.8] | 8.3 ± 3.8 [0.5:18.3] | 12.7 ± 4.5 [5.2:34.1] | 4.4 ± 2.2 [2.1:18.2]
Ctrough (microgram per mL) | 0.45 ± 0.26 [0.05:2.34] | 0.05 ± 0.13 [0.01:0.92] | 0.14 ± 0.25 [0.04:1.94] | 0.10 ± 0.08 [0.04:0.58]
SD=Standard Deviation

Specific Populations

Geriatric Patients

The pharmacokinetics of elvitegravir, cobicistat, emtricitabine, and tenofovir have not been fully evaluated in elderly (65 years of age and older) patients [see Use in Specific Populations (8.5)].

Pediatric Patients

Exposures (AUC) of elvitegravir and tenofovir in 14 pediatric subjects aged 12 to less than 18 years who received STRIBILD in Study 112 were increased by 30% and 37%, respectively, compared with exposures achieved in adults following administration of STRIBILD, but were deemed acceptable based on the overall safety profile of these agents and exposure-safety assessments. The other components of STRIBILD had similar exposures in adolescents compared with adults [see Use in Specific Populations (8.4)].

Emtricitabine has been studied in pediatric subjects from 3 months to 17 years of age. TDF has been studied in pediatric subjects from 2 years to less than 18 years of age. The pharmacokinetics of elvitegravir or cobicistat in pediatric subjects less than 12 years of age have not been established [see Use in Specific Populations (8.4)].

Race, Gender

No clinically significant differences in pharmacokinetics of STRIBILD have been identified based on race or gender.

Patients with Renal Impairment

Elvitegravir and Cobicistat: A study of the pharmacokinetics of cobicistat+elvitegravir was performed in healthy subjects and subjects with severe renal impairment (estimated creatinine clearance less than 30 mL per minute). No clinically relevant differences in elvitegravir or cobicistat pharmacokinetics were observed between healthy subjects and subjects with severe renal impairment.

Emtricitabine and TDF: The pharmacokinetics of emtricitabine and tenofovir are altered in subjects with estimated creatinine clearance below 50 mL per minute or with end-stage renal disease requiring dialysis (ESRD) (Table 8) [see Warnings and Precautions (5.2) and Use in Specific Populations (8.6)].

Table 8 Pharmacokinetic Parameters of Emtricitabine [200 mg, single dose of emtricitabine] and Tenofovir [300 mg, single dose of TDF] in Adults with Varying Degrees of Renal Function
Parameter Mean ± SD | Creatinine Clearance (mL/min)
Parameter Mean ± SD | >80 | 50–80 | 30–49 | <30 | ESRD [ESRD subjects requiring dialysis]
Emtricitabine | N=6 | N=6 | N=6 | N=5 | N=5
AUCinf (microgram∙hr per mL) | 11.8 ± 2.9 | 19.9 ± 1.2 | 25.1 ± 5.7 | 33.7± 2.1 | 53.2 ± 9.9
Cmax (microgram per mL) | 2.2 ± 0.6 | 3.8 ± 0.9 | 3.2 ± 0.6 | 2.8 ± 0.7 | 2.8 ± 0.5
Tenofovir | N=3 | N=10 | N=8 | N=11 | N=9
AUCinf (microgram∙hr per mL) | 2.18 ± 0.26 | 3.06 ± 0.93 | 6.01 ± 2.50 | 15.98 ± 7.22 | 44.90 ± 12.96
Cmax (microgram per mL) | 0.34 ± 0.03 | 0.33 ± 0.06 | 0.37 ± 0.16 | 0.60 ± 0.19 | 1.06 ± 0.25
SD=Standard Deviation

Patients with Hepatic Impairment

Elvitegravir and Cobicistat: A study of the pharmacokinetics of cobicistat+elvitegravir was performed in healthy subjects and subjects with moderate hepatic impairment (Child-Pugh Class B). No clinically relevant differences in elvitegravir or cobicistat pharmacokinetics were observed between subjects with moderate hepatic impairment and healthy subjects. The effect of severe hepatic impairment (Child-Pugh Class C) on the pharmacokinetics of elvitegravir or cobicistat has not been studied [see Use in Specific Populations (8.7)].

Emtricitabine: The pharmacokinetics of emtricitabine have not been studied in subjects with hepatic impairment; however, emtricitabine is not significantly metabolized by liver enzymes, so the impact of liver impairment should be limited.

Tenofovir DF: The pharmacokinetics of tenofovir following a 300 mg dose of VIREAD have been studied in healthy subjects with moderate to severe hepatic impairment (Child-Pugh Class C). No clinically relevant differences in tenofovir pharmacokinetics were observed between subjects with hepatic impairment and healthy subjects.

Hepatitis B and/or Hepatitis C Virus Coinfection

Elvitegravir: Limited data from population pharmacokinetic analysis (N=24) indicated that hepatitis B and/or C virus infection had no clinically relevant effect on the exposure of cobicistat-boosted elvitegravir.

Cobicistat: There were insufficient pharmacokinetic data in the clinical trials to determine the effect of hepatitis B and/or C virus infection on the pharmacokinetics of cobicistat.

Emtricitabine and TDF: The pharmacokinetics of emtricitabine and TDF have not been fully evaluated in subjects coinfected with hepatitis B and/or C virus.

Assessment of Drug Interactions

[see Contraindications (4) and Drug Interactions (7)]

The drug-drug interaction studies described were conducted with STRIBILD, elvitegravir (coadministered with cobicistat or RTV), or cobicistat administered alone.

As STRIBILD is indicated for use as a complete regimen for the treatment of HIV-1 infection and should not be administered with other antiretroviral medications, information regarding drug-drug interactions with other antiretroviral agents is not provided.

The effects of coadministered drugs on the exposure of elvitegravir, emtricitabine, and tenofovir are shown in Table 9, Table 10, and Table 11 respectively. The effects of elvitegravir plus cobicistat, or cobicistat, or emtricitabine on the exposure of coadministered drugs are shown in Table 12. For information regarding clinical recommendations, [see Drug Interactions (7)].

Table 9 Drug Interactions: Changes in Pharmacokinetic Parameters for Elvitegravir in the Presence of the Coadministered Drug [All interaction studies conducted in healthy volunteers.]
Coadministered Drug | Dose of Coadministered Drug | Elvitegravir Dose (mg) | Cobicistat or RTV Booster Dose (mg) | N | Mean Ratio of Elvitegravir Pharmacokinetic Parameters (90% CI); No Effect=1.00
Coadministered Drug | Dose of Coadministered Drug | Elvitegravir Dose (mg) | Cobicistat or RTV Booster Dose (mg) | N | Cmax | AUC | Cmin
Maximum strength antacid [Maximum strength antacid contained 80 mg aluminum hydroxide, 80 mg magnesium hydroxide, and 8 mg simethicone, per mL.] | 20 mL single dose given 4 hours before elvitegravir | 50 single dose | RTV 100 single dose | 8 | 0.95 (0.84, 1.07) | 0.96 (0.88, 1.04) | 1.04 (0.93, 1.17)
Maximum strength antacid [Maximum strength antacid contained 80 mg aluminum hydroxide, 80 mg magnesium hydroxide, and 8 mg simethicone, per mL.] | 20 mL single dose given 4 hours after elvitegravir | 50 single dose | RTV 100 single dose | 10 | 0.98 (0.88, 1.10) | 0.98 (0.91, 1.06) | 1.00 (0.90, 1.11)
Maximum strength antacid [Maximum strength antacid contained 80 mg aluminum hydroxide, 80 mg magnesium hydroxide, and 8 mg simethicone, per mL.] | 20 mL single dose given 2 hours before elvitegravir | 50 single dose | RTV 100 single dose | 11 | 0.82 (0.74, 0.91) | 0.85 (0.79, 0.91) | 0.90 (0.82, 0.99)
Maximum strength antacid [Maximum strength antacid contained 80 mg aluminum hydroxide, 80 mg magnesium hydroxide, and 8 mg simethicone, per mL.] | 20 mL single dose given 2 hours after elvitegravir | 50 single dose | RTV 100 single dose | 10 | 0.79 (0.71, 0.88) | 0.80 (0.75, 0.86) | 0.80 (0.73, 0.89)
Atorvastatin | 10 mg single dose | 150 once daily [Study conducted with GENVOYA® (elvitegravir/cobicistat/emtricitabine/tenofovir alafenamide).] | Cobicistat 150 once daily | 16 | 0.91 (0.85, 0.98) | 0.92 (0.87, 0.98) | 0.88 (0.81, 0.96)
Carbamazepine | 200 mg twice daily | 150 once daily | Cobicistat 150 once daily | 12 | 0.55 (0.49, 0.61) | 0.31 (0.28, 0.33) | 0.03 (0.02, 0.04)
Famotidine | 40 mg once daily given 12 hours after elvitegravir | 150 once daily | Cobicistat 150 once daily | 10 | 1.02 (0.89, 1.17) | 1.03 (0.95, 1.13) | 1.18 (1.05, 1.32)
Famotidine | 40 mg once daily given simultaneously with elvitegravir | 150 once daily | Cobicistat 150 once daily | 16 | 1.00 (0.92, 1.10) | 1.03 (0.98, 1.08) | 1.07 (0.98, 1.17)
Ketoconazole | 200 mg twice daily | 150 once daily | RTV 100 once daily | 18 | 1.17 (1.04, 1.33) | 1.48 (1.36, 1.62) | 1.67 (1.48, 1.88)
Ledipasvir/Sofosbuvir | 90/400 mg once daily | 150 once daily | Cobicistat 150 once daily [Percent change of cobicistat PK parameters (90% CI) was 1.25 (1.18 to 1.32) for Cmax, 1.59 (1.49 to 1.70) for AUC, and 4.25 (3.47 to 5.22) for Cmin.] | 29 | 0.88 (0.82, 0.95) | 1.02 (0.95, 1.09) | 1.36 (1.23, 1.49)
Omeprazole | 40 mg once daily given 2 hours before elvitegravir | 50 once daily | RTV 100 once daily | 9 | 0.93 (0.83, 1.04) | 0.99 (0.91, 1.07) | 0.94 (0.85, 1.04)
Omeprazole | 20 mg once daily given 2 hours before elvitegravir | 150 once daily | Cobicistat 150 once daily | 11 | 1.16 (1.04, 1.30) | 1.10 (1.02, 1.19) | 1.13 (0.96, 1.34)
Omeprazole | 20 mg once daily given 12 hours after elvitegravir | 150 once daily | Cobicistat 150 once daily | 11 | 1.03 (0.92, 1.15) | 1.05 (0.93, 1.18) | 1.10 (0.92, 1.32)
Rifabutin | 150 mg once every other day | 150 once daily | Cobicistat 150 once daily | 12 | 0.91 (0.84, 0.99) | 0.79 (0.74, 0.85) | 0.33 (0.27, 0.40)
Rosuvastatin | 10 mg single dose | 150 once daily | Cobicistat 150 once daily | 10 | 0.94 (0.83, 1.07) | 1.02 (0.91, 1.14) | 0.98 (0.83, 1.16)
Sertraline | 50 mg single dose | 150 once daily | Cobicistat 150 once daily | 19 | 0.88 (0.82, 0.93) | 0.94 (0.89, 0.98) | 0.99 (0.93, 1.05)
Sofosbuvir/Velpatasvir | 400/100 mg once daily | 150 once daily [Study conducted with STRIBILD.] | Cobicistat 150 once daily, [Percent change of cobicistat PK parameters (90% CI) was1.11 (1.06, 1.17) for Cmax, 1.23 (1.17, 1.29) for AUC, and 1.71 (1.54, 1.90) for Cmin.] | 24 | 0.93 (0.86, 1.00) | 0.93 (0.87, 0.99) | 0.97 (0.91, 1.04)
Sofosbuvir/Velpatasvir Voxilaprevir | 400/100/100 + 100 Voxilaprevir once daily [Study conducted with additional voxilaprevir 100 mg to achieve voxilaprevir exposures expected in HCV-infected patients.] | 150 once daily | Cobicistat 150 once daily | 29 | 0.79 (0.75, 0.85) | 0.94 (0.88, 1.00) | 1.32 (1.17, 1.49)

Table 10 Drug Interactions: Changes in Pharmacokinetic Parameters for Emtricitabine in the Presence of the Coadministered Drug [All interaction studies conducted in healthy volunteers.]
Coadministered Drug | Dose of Coadministered Drug (mg) | Emtricitabine Dose (mg) | N | Mean Ratio of Emtricitabine Pharmacokinetic Parameters (90%CI); No Effect=1.00
Coadministered Drug | Dose of Coadministered Drug (mg) | Emtricitabine Dose (mg) | N | Cmax | AUC | Cmin
Famciclovir | 500 single dose | 200 single dose | 12 | 0.90 (0.80, 1.01) | 0.93 (0.87, 0.99) | NC
NC=Not calculated

Table 11 Drug Interactions: Changes in Pharmacokinetic Parameters for Tenofovir in the Presence of the Coadministered Drug [All interaction studies conducted in healthy volunteers.]
Coadministered Drug | Dose of Coadministered Drug (mg) | TDF Dose (mg) | N | Mean Ratio of Tenofovir Pharmacokinetic Parameters (90%CI); No Effect=1.00
Coadministered Drug | Dose of Coadministered Drug (mg) | TDF Dose (mg) | N | Cmax | AUC | Cmin
Sofosbuvir/Velpatasvir | 400/100 once daily | 300 once daily [Study conducted with STRIBILD.] | 24 | 1.36 (1.25, 1.47) | 1.35 (1.29, 1.42) | 1.45 (1.39, 1.51)

Table 12 Drug Interactions: Changes in Pharmacokinetic Parameters for Coadministered Drug in the Presence of Elvitegravir plus Cobicistat, Cobicistat, Emtricitabine, or STRIBILD [All interaction studies conducted in healthy volunteers.]
Coadministered Drug | Dose of Coadministered Drug (mg) | Elvitegravir Dose [NA=Not Applicable] (mg) | Cobicistat Booster Dose (mg) | FTC Dose (mg) | N | Mean Ratio of Coadministered Drug Pharmacokinetic Parameters [NC=Not Calculated] (90% CI); No Effect=1.00
Coadministered Drug | Dose of Coadministered Drug (mg) | Elvitegravir Dose [NA=Not Applicable] (mg) | Cobicistat Booster Dose (mg) | FTC Dose (mg) | N | Cmax | AUC | Cmin
Atorvastatin | 10 single dose | 150 once daily [Study conducted with GENVOYA.] | 150 once daily | 200 once daily | 16 | 2.32 (1.91, 2.82) | 2.60 (2.31, 2.93) | NC
Buprenorphine | 16–24 once daily | 150 once daily | 150 once daily | NA | 17 | 1.12 (0.98, 1.27) | 1.35 (1.18, 1.55) | 1.66 (1.43, 1.93)
Norbuprenorphine | 16–24 once daily | 150 once daily | 150 once daily | NA | 17 | 1.24 (1.03, 1.49) | 1.42 (1.22, 1.67) | 1.57 (1.31, 1.88)
Carbamazepine | 200 twice daily | 150 once daily | 150 once daily | NA | 12 | 1.40 (1.32, 1.49) | 1.43 (1.36, 1.52) | 1.51 (1.41, 1.62)
Carbamazepine-10,11-epoxide | 200 twice daily | 150 once daily | 150 once daily | NA | 12 | 0.73 (0.70, 0.78) | 0.65 (0.63, 0.66) | 0.59 (0.57, 0.61)
Desipramine | 50 single dose | NA | 150 once daily | NA | 8 | 1.24 (1.08, 1.44) | 1.65 (1.36, 2.02) | NC
Digoxin | 0.5 single dose | NA | 150 once daily | NA | 22 | 1.41 (1.29, 1.55) | 1.08 (1.00, 1.17) | NC
Famciclovir | 500 single dose | NA | NA | 200 single dose | 12 | 0.93 (0.78, 1.11) | 0.91 (0.84, 0.99) | NC
Ledipasvir | 90/400 once daily | 150 once daily | 150 once daily | NA | 29 | 1.63 (1.51, 1.75) | 1.78 (1.64, 1.94) | 1.91 (1.76, 2.08)
Sofosbuvir | 90/400 once daily | 150 once daily | 150 once daily | NA | 29 | 1.33 (1.14, 1.56) | 1.36 (1.21, 1.52) | NA
GS-331007 [The predominant circulating nucleoside metabolite of sofosbuvir.] | 90/400 once daily | 150 once daily | 150 once daily | NA | 29 | 1.33 (1.22, 1.44) | 1.44 (1.41, 1.48) | 1.53 (1.47, 1.59)
Naloxone | 4–6 once daily | 150 once daily | 150 once daily | NA | 17 | 0.72 (0.61, 0.85) | 0.72 (0.59, 0.87) | NA
Norgestimate/ ethinyl estradiol | 0.180/0.215/ 0.250 norgestimate once daily | 150 once daily [Study conducted with STRIBILD.] | 150 once daily | 200 once daily | 13 | 2.08 (2.00, 2.17) | 2.26 (2.15, 2.37) | 2.67 (2.43, 2.92)
Norgestimate/ ethinyl estradiol | 0.025 ethinyl estradiol once daily | 150 once daily [Study conducted with STRIBILD.] | 150 once daily | 200 once daily | 13 | 0.94 (0.86, 1.04) | 0.75 (0.69, 0.81) | 0.56 (0.52, 0.61)
R-Methadone | 80–120 daily | 150 once daily | 150 once daily | NA | 11 | 1.01 (0.91, 1.13) | 1.07 (0.96, 1.19) | 1.10 (0.95, 1.28)
S-Methadone | 80–120 daily | 150 once daily | 150 once daily | NA | 11 | 0.96 (0.87, 1.06) | 1.00 (0.89, 1.12) | 1.02 (0.89, 1.17)
Sofosbuvir | 400/100 once daily | 150 once daily | 150 once daily | 200 once daily | 24 | 1.01 (0.85, 1.19) | 1.24 (1.13, 1.37) | NA
GS-331007 | 400/100 once daily | 150 once daily | 150 once daily | 200 once daily | 24 | 1.13 (1.07, 1.18) | 1.35 (1.30, 1.40) | 1.45 (1.38, 1.52)
Velpatasvir | 400/100 once daily | 150 once daily | 150 once daily | 200 once daily | 24 | 1.05 (0.93, 1.19) | 1.19 (1.07, 1.34) | 1.37 (1.22, 1.54)
Sofosbuvir | 400/100/100 + 100 Voxilaprevir [Study conducted with additional voxilaprevir 100 mg to achieve voxilaprevir exposures expected in HCV-infected patients] once daily | 150 once daily | 150 once daily | 200 once daily | 29 | 1.27 (1.09, 1.48) | 1.22 (1.12, 1.32) | NC
GS-331007 | 400/100/100 + 100 Voxilaprevir [Study conducted with additional voxilaprevir 100 mg to achieve voxilaprevir exposures expected in HCV-infected patients] once daily | 150 once daily | 150 once daily | 200 once daily | 29 | 1.28 (1.25, 1.32) | 1.43 (1.39, 1.47) | NC
Velpatasvir | 400/100/100 + 100 Voxilaprevir [Study conducted with additional voxilaprevir 100 mg to achieve voxilaprevir exposures expected in HCV-infected patients] once daily | 150 once daily | 150 once daily | 200 once daily | 29 | 0.96 (0.89, 1.04) | 1.16 (1.06, 1.27) | 1.46 (1.30, 1.64)
Voxilaprevir | 400/100/100 + 100 Voxilaprevir [Study conducted with additional voxilaprevir 100 mg to achieve voxilaprevir exposures expected in HCV-infected patients] once daily | 150 once daily | 150 once daily | 200 once daily | 29 | 1.92 (1.63, 2.26) | 2.71 (2.30, 3.19) | 4.50 (3.68, 5.50)
Rifabutin | 150 once every other day | 150 once daily | 150 once daily | NA | 12 | 1.09 (0.98, 1.20) [Comparison based on rifabutin 300 mg once daily.] | 0.92 (0.83, 1.03) | 0.94 (0.85, 1.04)
25-O-desacetyl-rifabutin | 150 once every other day | 150 once daily | 150 once daily | NA | 12 | 4.84 (4.09, 5.74) | 6.25 (5.08, 7.69) | 4.94 (4.04, 6.04)
Rosuvastatin | 10 single dose | 150 once daily | 150 single dose | NA | 10 | 1.89 (1.48, 2.42) | 1.38 (1.14, 1.67) | NC
Sertraline | 50 single dose | 150 once daily | 150 once daily | 200 once daily | 19 | 1.14 (0.94, 1.38) | 0.93 (0.77, 1.13) | NA
FTC=emtricitabine

12.4 Microbiology

Mechanism of Action

Elvitegravir: Elvitegravir inhibits the strand transfer activity of HIV-1 integrase (integrase strand transfer inhibitor; INSTI), an HIV-1 encoded enzyme that is required for viral replication. Inhibition of integrase prevents the integration of HIV-1 DNA into host genomic DNA, blocking the formation of the HIV-1 provirus and propagation of the viral infection. Elvitegravir does not inhibit human topoisomerases I or II.

Cobicistat: Cobicistat is a selective, mechanism-based inhibitor of cytochromes P450 of the CYP3A subfamily. Inhibition of CYP3A-mediated metabolism by cobicistat enhances the systemic exposure of CYP3A substrates, such as elvitegravir, where bioavailability is limited and half-life is shortened by CYP3A-dependent metabolism.

Emtricitabine: Emtricitabine, a synthetic nucleoside analog of cytidine, is phosphorylated by cellular enzymes to form emtricitabine 5'-triphosphate. Emtricitabine 5'-triphosphate inhibits the activity of the HIV-1 RT by competing with the natural substrate deoxycytidine 5'-triphosphate and by being incorporated into nascent viral DNA, which results in chain termination. Emtricitabine 5'-triphosphate is a weak inhibitor of mammalian DNA polymerases α, β, ε, and mitochondrial DNA polymerase γ.

Tenofovir DF: Tenofovir DF is an acyclic nucleoside phosphonate diester analog of adenosine monophosphate. Tenofovir DF requires initial diester hydrolysis for conversion to tenofovir and subsequent phosphorylations by cellular enzymes to form tenofovir diphosphate. Tenofovir diphosphate inhibits the activity of HIV-1 RT by competing with the natural substrate deoxyadenosine 5'-triphosphate and, after incorporation into DNA, by DNA chain termination. Tenofovir diphosphate is a weak inhibitor of mammalian DNA polymerases α, β, and mitochondrial DNA polymerase γ.

Antiviral Activity in Cell Culture

Elvitegravir, Cobicistat, Emtricitabine, and TDF: The triple combination of elvitegravir, emtricitabine, and tenofovir was not antagonistic in cell culture combination antiviral activity assays and was not affected by the addition of cobicistat.

Elvitegravir: The antiviral activity of elvitegravir against laboratory and clinical isolates of HIV-1 was assessed in T lymphoblastoid cell lines, monocyte/macrophage cells, and primary peripheral blood lymphocytes. The 50% effective concentrations (EC50) ranged from 0.02 to 1.7 nM. Elvitegravir displayed antiviral activity in cell culture against HIV-1 clades A, B, C, D, E, F, G, and O (EC50 values ranged from 0.1 to 1.3 nM) and activity against HIV-2 (EC50 value of 0.53 nM). Elvitegravir did not show inhibition of replication of HBV or HCV in cell culture.

Cobicistat: Cobicistat has no detectable antiviral activity in cell culture against HIV-1, HBV, or HCV and does not antagonize the antiviral activity of elvitegravir, emtricitabine, or tenofovir.

Emtricitabine: The antiviral activity of emtricitabine against laboratory and clinical isolates of HIV-1 was assessed in T lymphoblastoid cell lines, the MAGI-CCR5 cell line, and primary peripheral blood mononuclear cells. The EC50 values for emtricitabine were in the range of 0.0013–0.64 micromolar. Emtricitabine displayed antiviral activity in cell culture against HIV-1 clades A, B, C, D, E, F, and G (EC50 values ranged from 0.007–0.075 micromolar) and showed strain-specific activity against HIV-2 (EC50 values ranged from 0.007–1.5 micromolar).

Tenofovir DF: The antiviral activity of tenofovir against laboratory and clinical isolates of HIV-1 was assessed in T lymphoblastoid cell lines, primary monocyte/macrophage cells and peripheral blood lymphocytes. The EC50 values for tenofovir were in the range of 0.04–8.5 micromolar. Tenofovir displayed antiviral activity in cell culture against HIV-1 clades A, B, C, D, E, F, G, and O (EC50 values ranged from 0.5–2.2 micromolar) and showed strain-specific activity against HIV-2 (EC50 values ranged from 1.6–5.5 micromolar).

Resistance

In Cell Culture

Elvitegravir: HIV-1 isolates with reduced susceptibility to elvitegravir have been selected in cell culture. Reduced susceptibility to elvitegravir was associated with the primary integrase substitutions T66A/I, E92G/Q, S147G, and Q148R. Additional integrase substitutions observed in cell-culture selection included D10E, S17N, H51Y, F121Y, S153F/Y, E157Q, D232N, R263K, and V281M.

Emtricitabine and TDF: HIV-1 isolates with reduced susceptibility to emtricitabine or tenofovir have been selected in cell culture. Reduced susceptibility to emtricitabine was associated with M184V/I substitutions in HIV-1 RT. HIV-1 isolates selected by tenofovir expressed a K65R substitution in HIV-1 RT and showed a 2–4 fold reduction in susceptibility to tenofovir.

In Clinical Studies

Elvitegravir: Development of substitutions T66A/I/K, E92G/Q, T97A, S147G, Q148H/K/R, and N155H in the HIV-1 integrase protein was primarily associated with resistance to elvitegravir. In addition to these primary elvitegravir resistance-associated substitutions, E92A, F121C/Y, P145S, Q146I/L/R, and N155S were also occasionally observed and were shown to confer reduced susceptibility to elvitegravir. In virus isolates harboring the observed primary elvitegravir resistance-associated substitutions, additional substitutions in integrase were detected including H51Y, L68I/V, G70R, V72A/N, I73V, Q95K/R, S119R, E138A/K, G140A/C/S, E157Q, K160N, E170A, S230R, and D232N.

Emtricitabine and TDF: HIV-1 isolates with reduced susceptibility to emtricitabine or tenofovir have been selected in subjects experiencing virologic failure in clinical trials. Genotypic analysis of these isolates identified the M184V/I and K65R amino acid substitutions in the viral RT, respectively.

Elvitegravir, Cobicistat, Emtricitabine, and TDF: In clinical trials of HIV-1-infected subjects with no antiretroviral treatment history, Studies 102 and 103 [see Clinical Studies (14)], by Week 144, the development of one or more primary substitutions associated with resistance to elvitegravir, emtricitabine, and/or tenofovir was observed in viruses from 51% (18/35) of the STRIBILD-treatment failure subjects with evaluable genotypic resistance data who received at least 8 weeks of STRIBILD and had HIV-1 RNA greater than or equal to 400 copies per mL at confirmed virologic failure, the end of each study year, or the time of early study drug discontinuation. The most common substitutions that emerged were M184V/I (N=17) in HIV-1 RT and the primary elvitegravir resistance-associated substitutions, E92Q (N=9), N155H (N=5), Q148R (N=3), T66I (N=2), and T97A (N=1) in integrase; K65R in RT was also detected (N=5). In virus isolates harboring the observed primary elvitegravir resistance substitutions, additional substitutions in integrase were detected including H51Y, L68I/V, G70R, I73V, G140C, S153A, E157Q, and G163R. The virus in all subjects with evaluable data for RT and IN and whose virus developed integrase substitutions associated with elvitegravir resistance (N=14) also developed the M184I/V RT substitutions, and had reduced susceptibility to both elvitegravir and emtricitabine. In phenotypic analyses, HIV-1 isolates expressing M184V/I RT substitutions showed reduced susceptibility to emtricitabine (42- to greater than 152-fold); those expressing the primary elvitegravir resistance-associated integrase substitutions showed reduced susceptibility to elvitegravir (4- to greater than 198-fold); and those expressing the K65R RT substitution showed reduced susceptibility to tenofovir (0.8- to 1.6-fold), compared to wild-type reference HIV-1.

There was an insufficient number of virologic failures with evaluable data (N=1) in clinical trials of virologically suppressed HIV-1-infected subjects with no history of virologic failure, studies 115 and 121, [see Clinical Studies (14)] to draw conclusions about the development of resistance.

Cross-Resistance

STRIBILD-treatment failure subject isolates exhibited varying degrees of cross-resistance within the INSTI and NRTI drug classes depending on the specific substitutions observed. These isolates remained susceptible to all NNRTIs and protease inhibitors.

Elvitegravir: Cross-resistance has been observed among INSTIs. Elvitegravir-resistant viruses showed varying degrees of cross-resistance in cell culture to raltegravir depending on the type and number of substitutions in HIV-1 integrase. Of the primary elvitegravir resistance-associated substitutions tested (T66A/I/K, E92G/Q, T97A, S147G, Q148H/K/R, and N155H), all but three (T66I, E92G, and S147G) conferred greater than 1.5-fold reduced susceptibility to raltegravir (above the biological cutoff for raltegravir) when introduced individually into a wild-type virus by site-directed mutagenesis. Of the primary raltegravir resistance-associated substitutions (Y143C/H/R, Q148H/K/R, and N155H), all but Y143C/H conferred greater than 2.5-fold reductions in susceptibility to elvitegravir (above the biological cutoff for elvitegravir).

Emtricitabine: Cross-resistance has been observed among NRTIs. Emtricitabine-resistant isolates harboring an M184V/I substitution in HIV-1 RT were cross-resistant to lamivudine. HIV-1 isolates containing the K65R RT substitution, selected in vivo by abacavir, didanosine, and tenofovir, demonstrated reduced susceptibility to inhibition by emtricitabine.

Tenofovir DF: Cross-resistance has been observed among NRTIs. The K65R substitution in HIV-1 RT selected by tenofovir is also selected in some HIV-1-infected patients treated with abacavir or didanosine. HIV-1 isolates with the K65R substitution also showed reduced susceptibility to emtricitabine and lamivudine. Therefore, cross-resistance among these NRTIs may occur in patients whose virus harbors the K65R substitution. The K70E substitution selected clinically by TDF results in reduced susceptibility to abacavir, didanosine, emtricitabine, lamivudine, and tenofovir. HIV-1 isolates from patients (N=20) whose HIV-1 expressed a mean of 3 zidovudine-associated RT amino acid substitutions (M41L, D67N, K70R, L210W, T215Y/F, or K219Q/E/N) showed a 3.1-fold decrease in the susceptibility to tenofovir. Subjects whose virus expressed an L74V RT substitution without zidovudine resistance-associated substitutions (N=8) had reduced response to TDF. Limited data are available for patients whose virus expressed a Y115F substitution (N=3), Q151M substitution (N=2), or T69 insertion (N=4) in HIV-1 RT, all of whom had a reduced response in clinical trials.

13 NONCLINICAL TOXICOLOGY

13.1 Carcinogenesis, Mutagenesis, Impairment of Fertility

Elvitegravir: Long-term carcinogenicity studies of elvitegravir were carried out in mice (104 weeks) and in rats for up to 88 weeks (males) and 90 weeks (females). No drug-related increases in tumor incidence were found in mice at doses up to 2000 mg per kg per day alone or in combination with 25 mg per kg per day RTV at exposures 3- and 14-fold, respectively, the human systemic exposure at the recommended daily dose of 150 mg. No drug-related increases in tumor incidence were found in rats at doses up to 2000 mg per kg per day at exposures 12- to 27-fold, respectively in male and female, the human systemic exposure.

Elvitegravir was not genotoxic in the reverse mutation bacterial test (Ames test) and the rat micronucleus assay. In an in vitro chromosomal aberration test, elvitegravir was negative with metabolic activation; however, an equivocal response was observed without activation.

Elvitegravir did not affect fertility in male and female rats at approximately 16- and 30-fold higher exposures (AUC), respectively, than in humans at the therapeutic 150 mg daily dose.

Fertility was normal in the offspring of rats exposed daily from before birth (in utero) through sexual maturity at daily exposures (AUC) of approximately 18-fold higher than human exposures at the recommended 150 mg daily dose.

Cobicistat: In a long-term carcinogenicity study in mice, no drug-related increases in tumor incidence were observed at doses up to 50 and 100 mg/kg/day (males and females, respectively). Cobicistat exposures at these doses were approximately 7 (male) and 16 (females) times, respectively, the human systemic exposure at the therapeutic daily dose. In a long-term carcinogenicity study of cobicistat in rats, an increased incidence of follicular cell adenomas and/or carcinomas in the thyroid gland was observed at doses of 25 and 50 mg/kg/day in males, and at 30 mg/kg/day in females. The follicular cell findings are considered to be rat-specific, secondary to hepatic microsomal enzyme induction and thyroid hormone imbalance, and are not relevant for humans. At the highest doses tested in the rat carcinogenicity study, systemic exposures were approximately 2 times the human systemic exposure at the therapeutic daily dose.

Cobicistat was not genotoxic in the reverse mutation bacterial test (Ames test), or the mouse lymphoma or rat micronucleus assays.

Cobicistat did not affect fertility in male or female rats at daily exposures (AUC) approximately 4-fold higher than human exposures at the recommended 150 mg daily dose.

Fertility was normal in the offspring of rats exposed daily from before birth (in utero) through sexual maturity at daily exposures (AUC) of approximately 1.2-fold higher than human exposures at the recommended 150 mg daily dose.

Emtricitabine: In long-term carcinogenicity studies of emtricitabine, no drug-related increases in tumor incidence were found in mice at doses up to 750 mg per kg per day (23 times the human systemic exposure at the therapeutic dose of 200 mg per day) or in rats at doses up to 600 mg per kg per day (28 times the human systemic exposure at the therapeutic dose).

Emtricitabine was not genotoxic in the reverse mutation bacterial test (Ames test), or the mouse lymphoma or mouse micronucleus assays.

Emtricitabine did not affect fertility in male rats at approximately 140-fold or in male and female mice at approximately 60-fold higher exposures (AUC) than in humans given the recommended 200 mg daily dose. Fertility was normal in the offspring of mice exposed daily from before birth (in utero) through sexual maturity at daily exposures (AUC) of approximately 60-fold higher than human exposures at the recommended 200 mg daily dose.

Tenofovir DF: Long-term oral carcinogenicity studies of TDF in mice and rats were carried out at exposures up to approximately 10 times (mice) and 4 times (rats) those observed in humans at the therapeutic dose for HIV-1 infection. At the high dose in female mice, liver adenomas were increased at exposures 10 times of that in humans. In rats, the study was negative for carcinogenic findings at exposures up to 4 times that observed in humans at the therapeutic dose.

Tenofovir DF was mutagenic in the in vitro mouse lymphoma assay and negative in an in vitro bacterial mutagenicity test (Ames test). In an in vivo mouse micronucleus assay, TDF was negative when administered to male mice.

There were no effects on fertility, mating performance or early embryonic development when TDF was administered to male rats at a dose equivalent to 10 times the human dose based on body-surface-area comparisons for 28 days prior to mating and to female rats for 15 days prior to mating through day seven of gestation. There was, however, an alteration of the estrous cycle in female rats.

14 CLINICAL STUDIES

14.1 Description of Clinical Trials

The efficacy and safety of STRIBILD were evaluated in the studies summarized in Table 13.

Table 13 Trials Conducted with STRIBILD in Subjects with HIV-1 Infection
Trial | Population | Study Arms (N) [Randomized and dosed.] | Timepoint (Week)
Study 102 [Randomized, double blind, active-controlled trial.] , [Patients had estimated creatinine clearance greater than or equal to 70 mL/min at screening.] | Adults with no antiretroviral treatment history | STRIBILD (348) ATRIPLA (352) | 144
Study 103 , | Adults with no antiretroviral treatment history | STRIBILD (353) TRUVADA+atazanavir+ritonavir (355) | 144
Study 115, [Randomized, open label, active-controlled trial.] | Virologically suppressed adults without a history of virologic failure [HIV-1 RNA less than 50 copies per mL.] | STRIBILD (293) TRUVADA+PI+ritonavir (140) | 48
Study 121, | Virologically suppressed adults without a history of virologic failure [HIV-1 RNA less than 50 copies per mL.] | STRIBILD (291) TRUVADA+NNRTI (143) | 48
Study 112 [Open label trial.] | Treatment-naïve adolescents between the ages of 12 to less than 18 years | STRIBILD (50) | 48

14.2 Clinical Trial Results in HIV-1 Infected Adult Subjects with No Antiretroviral Treatment History

In Study 102, subjects were randomized in a 1:1 ratio to receive either STRIBILD (N=348) once daily or ATRIPLA (N=352) once daily. The mean age was 38 years (range 18–67), 89% were male, 63% were White, 28% were Black, and 2% were Asian. Twenty-four percent of subjects identified as Hispanic/Latino. The mean baseline plasma HIV-1 RNA was 4.8 log10 copies per mL (range 2.6–6.5). The mean baseline CD4+ cell count was 386 cells per mm^3 (range 3–1348), and 13% had CD4+ cell counts less than 200 cells per mm^3. Thirty-three percent of subjects had baseline viral loads greater than 100,000 copies per mL.

In Study 103, subjects were randomized in a 1:1 ratio to receive either STRIBILD (N=353) once daily or ATV 300 mg + RTV 100 mg + TRUVADA (N=355) once daily. The mean age was 38 years (range 19–72), 90% were male, 74% were White, 17% were Black, and 5% were Asian. Sixteen percent of subjects identified as Hispanic/Latino. The mean baseline plasma HIV-1 RNA was 4.8 log10 copies per mL (range 1.7–6.6). The mean baseline CD4+ cell count was 370 cells per mm^3 (range 5–1132), and 13% had CD4+ cell count less than 200 cells per mm^3. Forty-one percent of subjects had baseline viral loads greater than 100,000 copies per mL.

In both studies, subjects were stratified by baseline HIV-1 RNA (less than or equal to 100,000 copies per mL or greater than 100,000 copies per mL).

Treatment outcomes of Study 102 and Study 103 through 144 weeks are presented in Table 14.

Table 14 Virologic Outcome of Randomized Treatment of Study 102 and Study 103 at Week 144 [Week-144 window is between Day 967 and 1050 (inclusive).]
 | Study 102 |  | Study 103
 | STRIBILD N=348 | ATRIPLA N=352 | STRIBILD N=353 | ATV+RTV+TRUVADA N=355
Virologic Success HIV-1 RNA <50 copies/mL | 80% | 75% | 78% | 75%
Treatment Difference | 4.9% (95% CI = −1.3%, 11.1%) |  | 3.1% (95% CI = −3.2%, 9.4%)
Virologic Failure [Includes subjects who had ≥50 copies/mL in the Week-144 window, subjects who discontinued early due to lack or loss of efficacy, subjects who discontinued for reasons other than an adverse event, death, or lack or loss of efficacy and at the time of discontinuation had a viral value of ≥50 copies/mL.] | 7% | 10% | 8% | 7%
No Virologic Data in Week 144 Window
Discontinued Study Drug Due to AE or Death [Includes patients who discontinued due to an adverse event or death at any time point from Day 1 through the time window if this resulted in no virologic data on treatment during the specified window.] | 6% | 8% | 6% | 8%
Discontinued Study Drug Due to Other Reasons and Last Available HIV-1 RNA <50 copies/mL [Includes subjects who discontinued for reasons other than an adverse event, death, or lack or loss of efficacy, e.g., withdrew consent, loss to follow-up, etc.] | 5% | 7% | 8% | 9%
Missing Data During Window but on Study Drug | 1% | 0% | 1% | 1%

In Study 102, the mean increase from baseline in CD4+ cell count at Week 144 was 298 cells per mm^3 in the STRIBILD-treated subjects and 272 cells per mm^3 in the ATRIPLA -treated subjects. In Study 103, the mean increase from baseline in CD4+ cell count at Week 144 was 261 cells per mm^3 in the STRIBILD-treated subjects and 269 cells per mm^3 in the ATV+RTV+TRUVADA-treated subjects.

14.3 Clinical Trial Results in Virologically Suppressed HIV-1 Infected Adult Subjects with No History of Virologic Failure

In Study 115, subjects had to be on either their first or second antiretroviral regimen with no history of virologic failure, with no current or past history of resistance to the antiretroviral components of STRIBILD, and must have been suppressed (HIV-1 RNA <50 copies/mL) on a ritonavir-boosted PI in combination with TRUVADA for at least 6 months prior to screening. Subjects were randomized in a 2:1 ratio to either switch to STRIBILD (STRIBILD arm, N=293; randomized and dosed) or stay on their baseline antiretroviral regimen for 48 weeks (PI+RTV+TRUVADA arm, N=140; randomized and dosed). Subjects had a mean age of 41 years (range 21–76), 86% were male, 80% were White, and 15% were Black. The mean baseline CD4+ cell count was 610 cells per mm^3 (range 74–1919). At screening subjects were receiving atazanavir (40%), darunavir (40%), lopinavir (17%), fosamprenavir (3%), or saquinavir (<1%) as the PI in their regimen.

In Study 121, subjects had to be on either their first or second antiretroviral regimen with no history of virologic failure, with no current or past history of resistance to the antiretroviral components of STRIBILD, and must have been suppressed (HIV-1 RNA <50 copies/mL) on a NNRTI in combination with TRUVADA for at least 6 months prior to screening. Subjects were randomized in a 2:1 ratio to either switch to STRIBILD (STRIBILD arm, N=291; randomized and dosed) or stay on their baseline antiretroviral regimen for 48 weeks (NNRTI+TRUVADA arm, N=143; randomized and dosed). Subjects had a mean age of 41 years (range 20–72); 93% were male, 78% were White, and 17% were Black. The mean baseline CD4+ cell count was 588 cells per mm^3 (range 100–1614). Randomization was stratified by use of efavirenz in the baseline regimen. At screening subjects were receiving efavirenz (78%) (predominantly as ATRIPLA [74%]), nevirapine (17%), rilpivirine (4%) (as COMPLERA® [4%]), or etravirine (1%) as the NNRTI in their regimen.

Virologic outcomes of Study 115 and Study 121 are presented in Table 15. Five treated subjects were excluded from the efficacy analysis: in Study 115, three STRIBILD subjects had protocol-prohibited documented resistance and one PI+RTV+TRUVADA subject was not on a protease inhibitor-based regimen at screening; in Study 121, one STRIBILD subject had protocol-prohibited documented resistance.

Table 15 Virologic Outcomes of Randomized Treatment in Study 115 and Study 121 at Week 48
 | Study GS-US-236-0115 [Week-48 window is between Day 295 and 378 (inclusive).] |  | Study GS-US-236-0121
 | STRIBILD N=290 | PI+RTV+TRUVADA N=139 | STRIBILD N=290 | NNRTI+TRUVADA N=143
Virologic Success HIV-1 RNA <50 copies/mL | 94% | 87% | 93% | 88%
Virologic Failure [Includes subjects who had ≥50 copies/mL in the Week-48 window, subjects who discontinued early due to lack or loss of efficacy, subjects who discontinued for reasons other than an adverse event, death, or lack or loss of efficacy and at the time of discontinuation had a viral value of ≥50 copies/mL.] | 1% | 1% | 1% | 1%
No Virologic Data in Week 48 Window | 6% | 12% | 6% | 11%
Discontinued Study Drug Due to AE or Death [Includes subjects who discontinued due to an adverse event or death at any time point from Day 1 through the time window if this resulted in no virologic data on treatment during the specified window.] | 2% | 1% | 2% | 1%
Discontinued Study Drug Due to Other Reasons and Last Available HIV-1 RNA <50 copies/mL [Includes subjects who discontinued for reasons other than an adverse event, death, or lack or loss of efficacy, e.g., withdrew consent, loss to follow-up, etc.] | 4% | 10% | 4% | 9%
Missing Data During Window but on Study Drug | 0% | 0% | 0% | 1%

14.4 Clinical Trial Results in HIV-1Treatment-Naïve Adolescent Subjects Aged 12 to Less than 18 Years

In Study 112, the efficacy, safety, and pharmacokinetics of STRIBILD were evaluated in a single group, open-label trial in HIV-1 infected treatment-naïve adolescents aged 12 to less than 18 years of age and weighing at least 35 kg (N=50). Mean age was 15 years (range 12–17); 70% were male, 68% black, and 28% Asian. At baseline, mean plasma HIV-1 RNA was 4.60 log10 copies per mL (range 3.18–5.73), mean CD4+ cell count was 399 cells per mm^3 (range 133–734), and mean CD4+ percentage was 20.9% (range 4.5%–41.1%). Twenty percent had baseline plasma HIV-1 RNA >100,000 copies per mL.

At Week 48, 44 of 50 (88%) adolescent patients treated with STRIBILD achieved HIV-1 RNA <50 copies per mL and 4 had HIV-1 RNA ≥50 copies per mL; 1 patient discontinued study drug; 1 had no virologic data at Week 48. The mean decrease from baseline in HIV-1 RNA was −3.16 log10 copies per mL; mean increase from baseline in CD4+ cell count was 229 cells per mm^3. No emergent resistance to STRIBILD was detected through Week 48.

16 HOW SUPPLIED/STORAGE AND HANDLING

STRIBILD tablets are green, capsule shaped, film coated, and debossed with "GSI" on one side and the number "1" surrounded by a square box () on the other side. Each bottle contains 30 tablets (NDC 61958-1201-1) and a silica gel desiccant, and is closed with a child-resistant closure.

STORAGE AND HANDLING

Store at 25 °C (77 °F), excursions permitted to 15–30 °C (59–86 °F) (see USP Controlled Room Temperature).

- Keep container tightly closed.
- Dispense only in original container.

17 PATIENT COUNSELING INFORMATION

Advise the patient to read the FDA-approved patient labeling (Patient Information).

Severe Acute Exacerbation of Hepatitis B in Patients Coinfected with HIV-1 and HBV

Inform patients that severe acute exacerbations of hepatitis B have been reported in patients who are coinfected with HBV and HIV-1 and have discontinued emtricitabine or TDF [see Warnings and Precautions (5.1)].

New Onset or Worsening Renal Impairment

Inform patients that renal impairment, including cases of acute renal failure and Fanconi syndrome, has been reported in association with the use of STRIBILD. Advise patients to avoid STRIBILD with concurrent or recent use of a nephrotoxic agent (e.g., high-dose or multiple NSAIDs) [see Warnings and Precautions (5.2)].

Lactic Acidosis and Severe Hepatomegaly

Inform patients that lactic acidosis and severe hepatomegaly with steatosis, including fatal cases, have been reported. Treatment with STRIBILD should be suspended in any patient who develops clinical symptoms suggestive of lactic acidosis or pronounced hepatotoxicity [see Warnings and Precautions (5.3)].

Drug Interactions

Advise patients that STRIBILD may interact with many drugs; therefore, advise patients to report to their healthcare provider the use of any other prescription or nonprescription medication or herbal products, including St. John's wort [see Contraindications (4), Warnings and Precautions (5.4) and Drug Interactions (7)].

Bone Loss and Mineralization Defects

Inform patients that decreases in bone mineral density have been observed with the use of STRIBILD. Assessment of bone mineral density (BMD) should be considered in patients who have a history of pathologic bone fracture or other risk factors for osteoporosis or bone loss [see Warnings and Precautions (5.5)].

Immune Reconstitution Syndrome

Inform patients that in some patients with advanced HIV infection (AIDS), signs and symptoms of inflammation from previous infections may occur soon after anti-HIV treatment is started. It is believed that these symptoms are due to an improvement in the body's immune response, enabling the body to fight infections that may have been present with no obvious symptoms. Advise patients to inform their healthcare provider immediately of any symptoms of infection [see Warnings and Precautions (5.6)].

Missed Dosage

Inform patients that it is important to take STRIBILD on a regular dosing schedule with food and to avoid missing doses as it can result in development of resistance [see Dosage and Administration (2.2)].

Pregnancy

Advise patients that STRIBILD is not recommended during pregnancy and to alert their healthcare provider if they become pregnant while taking STRIBILD [see Dosage and Administration (2.5) and Use in Specific Populations (8.1)]. Inform patients that there is an antiretroviral pregnancy registry to monitor fetal outcomes of pregnant individuals exposed to STRIBILD [see Use in Specific Populations (8.1)].

Lactation

Instruct mothers with HIV-1 infection not to breastfeed because HIV-1 can be passed to the baby in breast milk [see Use in Specific Populations (8.2)].

© 2021 Gilead Sciences, Inc. All rights reserved.

STRIBILD, ATRIPLA, COMPLERA, EMTRIVA, EPCLUSA, GENVOYA, HARVONI, TRUVADA, VIREAD, and VOSEVI are trademarks of Gilead Sciences, Inc., or its related companies. All other trademarks referenced herein are the property of their respective owners.

PATIENT INFORMATION
STRIBILD® (STRY-bild)
(elvitegravir, cobicistat, emtricitabine,
and tenofovir disoproxil fumarate)
tablets

Important: Ask your healthcare provider or pharmacist about medicines that should not be taken with STRIBILD. For more information, see the section "What should I tell my healthcare provider before taking STRIBILD?"

What is the most important information I should know about STRIBILD?

STRIBILD can cause serious side effects, including:

- Worsening of Hepatitis B infection. If you have hepatitis B virus (HBV) infection and take STRIBILD, your HBV may get worse (flare-up) if you stop taking STRIBILD. A "flare-up" is when your HBV infection suddenly returns in a worse way than before.
  - Do not run out of STRIBILD. Refill your prescription or talk to your healthcare provider before your STRIBILD is all gone.
  - Do not stop taking STRIBILD without first talking to your healthcare provider.
  - If you stop taking STRIBILD, your healthcare provider will need to check your health often and do blood tests regularly for several months to check your HBV infection. Tell your healthcare provider about any new or unusual symptoms you may have after you stop taking STRIBILD.

See "What are the possible side effects of STRIBILD?" for more information about side effects.

What is STRIBILD?

STRIBILD is a prescription medicine that is used without other antiretroviral medicines to treat Human Immunodeficiency Virus-1 (HIV-1) in people 12 years of age and older:

- who have not received anti-HIV-1 medicines in the past, or
- to replace their current anti-HIV-1 medicines:
  - in people who have been on the same anti-HIV-1 medicine regimen for at least 6 months, and
  - who have an amount of HIV-1 in their blood (this is called "viral load") that is less than 50 copies/mL, and
  - have never failed past HIV-1 treatment.

HIV-1 is the virus that causes AIDS (Acquired Immune Deficiency Syndrome).

STRIBILD contains the medicines elvitegravir, cobicistat, emtricitabine, and tenofovir disoproxil fumarate.

It is not known if STRIBILD is safe and effective in children under 12 years of age or who weigh less than 77 lbs.

Do not take STRIBILD if you also take a medicine that contains:

- alfuzosin hydrochloride
- carbamazepine
- ergot-containing medicines, including:
  - dihydroergotamine mesylate
  - ergotamine tartrate
  - methylergonovine maleate
- lomitapide
- lovastatin
- lurasidone
- midazolam, when taken by mouth
- phenobarbital
- phenytoin
- pimozide
- rifampin
- sildenafil, when used for treating the lung problem, pulmonary arterial hypertension (PAH)
- simvastatin
- triazolam
- St. John's wort (Hypericum perforatum) or a product that contains St. John's wort

What should I tell my healthcare provider before taking STRIBILD?

Before taking STRIBILD, tell your healthcare provider about all of your medical conditions, including if you:

- have liver problems including hepatitis B infection
- have kidney problems
- have bone problems
- are pregnant or plan to become pregnant.
  - It is not known if STRIBILD can harm your unborn baby.
  - STRIBILD should not be used during pregnancy because you may not have enough STRIBILD in your body during pregnancy.
  - Tell your healthcare provider if you become pregnant while taking STRIBILD. Your healthcare provider may prescribe different medicines if you become pregnant while taking STRIBILD.
  Pregnancy Registry. There is a pregnancy registry for women who take antiviral medicines during pregnancy. The purpose of this registry is to collect information about the health of you and your baby. Talk with your healthcare provider about how you can take part in this registry.
- are breastfeeding or plan to breastfeed. Do not breastfeed if you take STRIBILD.
  - You should not breastfeed if you have HIV-1 because of the risk of passing HIV-1 to your baby.
  - At least two of the medicines in STRIBILD can pass to your baby in your breast milk. It is not known if the other medicines in STRIBILD can pass into your breast milk.
  Talk with your healthcare provider about the best way to feed your baby.

Tell your healthcare provider about all the medicines you take, including prescription and over-the-counter medicines, vitamins, and herbal supplements.

Some medicines may interact with STRIBILD. Keep a list of your medicines and show it to your healthcare provider and pharmacist when you get a new medicine.

- You can ask your healthcare provider or pharmacist for a list of medicines that interact with STRIBILD.
- Do not start a new medicine without telling your healthcare provider. Your healthcare provider can tell you if it is safe to take STRIBILD with other medicines.

How should I take STRIBILD?

- Take STRIBILD exactly as your healthcare provider tells you to take it. STRIBILD is taken by itself (not with other anti-HIV-1 medicines) to treat HIV-1 infection.
- Take STRIBILD 1 time each day with food.
- Do not change your dose or stop taking STRIBILD without first talking with your healthcare provider. Stay under a healthcare provider's care when taking STRIBILD.
- If you need to take a medicine for indigestion (antacid) that contains aluminum and magnesium hydroxide or calcium carbonate during treatment with STRIBILD, take it at least 2 hours before or after you take STRIBILD.
- Do not miss a dose of STRIBILD.
- When your STRIBILD supply starts to run low, get more from your healthcare provider or pharmacy. This is very important because the amount of virus in your blood may increase if the medicine is stopped for even a short time. The virus may develop resistance to STRIBILD and become harder to treat.
- If you take too much STRIBILD, call your healthcare provider or go to the nearest hospital emergency room right away.

What are the possible side effects of STRIBILD?

STRIBILD may cause the following serious side effects, including:

- See "What is the most important information I should know about STRIBILD?"
- New or worse kidney problems, including kidney failure. Your healthcare provider should do blood and urine tests to check your kidneys before you start and while you are taking STRIBILD. Your healthcare provider may tell you to stop taking STRIBILD if you develop new or worse kidney problems.
- Too much lactic acid in your blood (lactic acidosis). Too much lactic acid is a serious but rare medical emergency that can lead to death. Tell your healthcare provider right away if you get these symptoms: weakness or being more tired than usual, unusual muscle pain, being short of breath or fast breathing, stomach pain with nausea and vomiting, cold or blue hands and feet, feel dizzy or lightheaded, or a fast or abnormal heartbeat.
- Severe liver problems. In rare cases, severe liver problems can happen that can lead to death. Tell your healthcare provider right away if you get these symptoms: skin or the white part of your eyes turns yellow, dark "tea-colored" urine, light-colored stools, loss of appetite for several days or longer, nausea, or stomach-area pain.
- Bone problems can happen in some people who take STRIBILD. Bone problems include bone pain, softening, or thinning (which may lead to fractures). Your healthcare provider may need to do tests to check your bones.
- Changes in your immune system (Immune Reconstitution Syndrome) can happen when you start taking HIV-1 medicines. Your immune system may get stronger and begin to fight infections that have been hidden in your body for a long time. Tell your healthcare provider right away if you start having any new symptoms after starting your HIV-1 medicine.

The most common side effects of STRIBILD include:

- nausea

- diarrhea

These are not all the possible side effects of STRIBILD.

Call your doctor for medical advice about side effects. You may report side effects to FDA at 1-800-FDA-1088.

How should I store STRIBILD?

- Store STRIBILD at room temperature between 68 °F to 77 °F (20 °C to 25 °C).
- The STRIBILD container contains a desiccant and has a child-resistant cap.
- Keep STRIBILD in its original container.
- Keep the container tightly closed.

Keep STRIBILD and all medicines out of reach of children.

General information about the safe and effective use of STRIBILD.

Medicines are sometimes prescribed for purposes other than those listed in a Patient Information leaflet. Do not use STRIBILD for a condition for which it was not prescribed. Do not give STRIBILD to other people, even if they have the same symptoms you have. It may harm them.

You can ask your healthcare provider or pharmacist for information about STRIBILD that is written for health professionals.

For more information, call 1-800-445-3235 or go to www.STRIBILD.com.

What are the ingredients in STRIBILD?

Active ingredients: elvitegravir, cobicistat, emtricitabine, and tenofovir disoproxil fumarate

Inactive ingredients: lactose monohydrate, microcrystalline cellulose, silicon dioxide, croscarmellose sodium, hydroxypropyl cellulose, sodium lauryl sulfate, and magnesium stearate. The tablets are film coated with a coating material containing indigo carmine (FD&C blue #2) aluminum lake, polyethylene glycol, polyvinyl alcohol, talc, titanium dioxide, and yellow iron oxide.

Manufactured and distributed by: Gilead Sciences, Inc. Foster City, CA 94404
STRIBILD is a trademark of Gilead Sciences, Inc., or its related companies.
For more information, call 1-800-445-3235 or go to www.STRIBILD.com
© 2021 Gilead Sciences, Inc. All rights reserved. 203100-GS-016

This Patient Information has been approved by the U.S. Food and Drug Administration.

Revised: 09/2021

PRINCIPAL DISPLAY PANEL - 30 Tablet Bottle Label

NDC 61958-1201-1
30 tablets

Stribild®

(elvitegravir, cobicistat,
emtricitabine, tenofovir
disoproxil fumarate) tablets
150 mg/150 mg/200 mg/300 mg

Note to pharmacist: Do not cover ALERT box with pharmacy label.

ALERT: Find out about medicines that
should NOT be taken with Stribild

Rx only